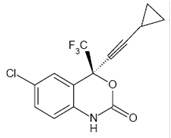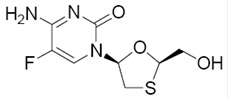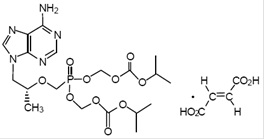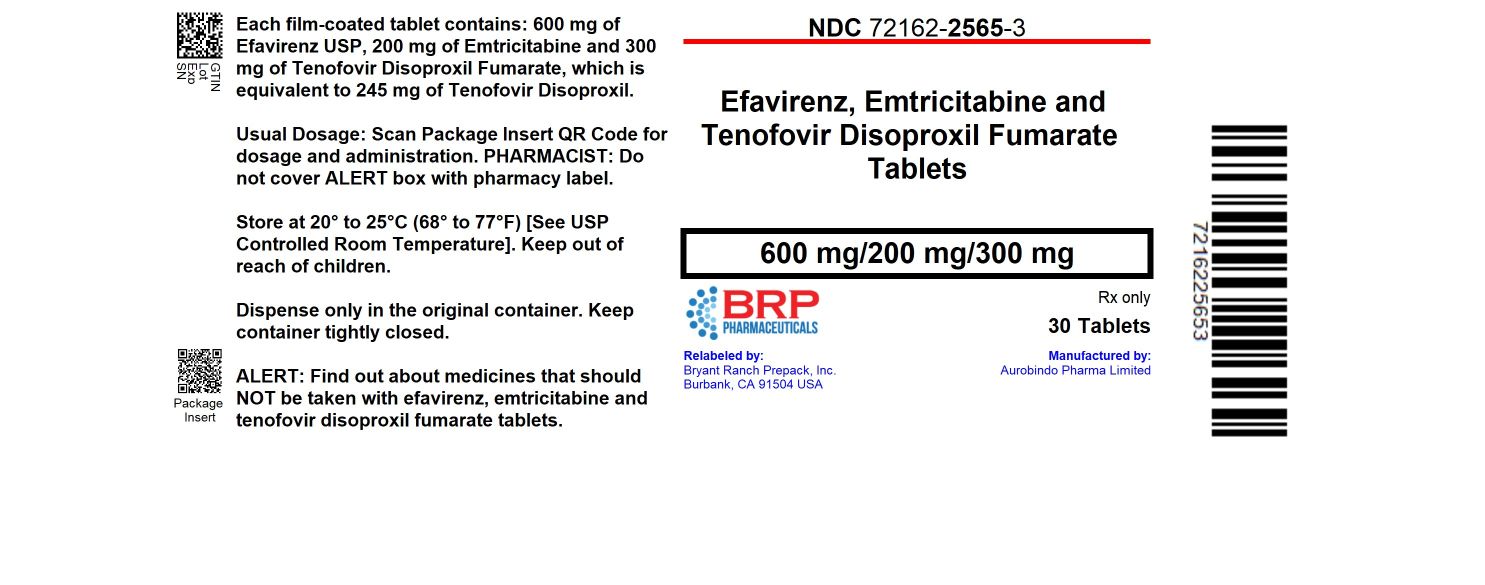 DRUG LABEL: Efavirenz, Emtricitabine And Tenofovir Disoproxil Fumarate
NDC: 72162-2565 | Form: TABLET, FILM COATED
Manufacturer: Bryant Ranch Prepack
Category: prescription | Type: HUMAN PRESCRIPTION DRUG LABEL
Date: 20251104

ACTIVE INGREDIENTS: EFAVIRENZ 600 mg/1 1; EMTRICITABINE 200 mg/1 1; TENOFOVIR DISOPROXIL FUMARATE 300 mg/1 1
INACTIVE INGREDIENTS: CROSCARMELLOSE SODIUM; HYDROXYPROPYL CELLULOSE (110000 WAMW); MAGNESIUM STEARATE; MICROCRYSTALLINE CELLULOSE 101; MICROCRYSTALLINE CELLULOSE 200; SODIUM LAURYL SULFATE; POLYETHYLENE GLYCOL 3350; POLYVINYL ALCOHOL, UNSPECIFIED; TALC; TITANIUM DIOXIDE

HIGHLIGHTS OF PRESCRIBING INFORMATION

These highlights do not include all the information needed to use EFAVIRENZ, EMTRICITABINE AND TENOFOVIR DISOPROXIL FUMARATE TABLETS safely and effectively. See full prescribing information for EFAVIRENZ, EMTRICITABINE AND TENOFOVIR DISOPROXIL FUMARATE TABLETS.
EFAVIRENZ, EMTRICITABINE and TENOFOVIR DISOPROXIL FUMARATE tablets, for oral use
Initial U.S. Approval: 2006

WARNING: POSTTREATMENT ACUTE EXACERBATION OF HEPATITIS B

WARNING: POSTTREATMENT ACUTE EXACERBATION OF
HEPATITIS B

See full prescribing information for complete boxed warning.

Severe acute exacerbations of hepatitis B virus (HBV) have been reported in patients coinfected with HBV and HIV-1 who have discontinued products containing emtricitabine (FTC) and/or tenofovir disoproxil fumarate (TDF), and may occur with discontinuation of efavirenz, emtricitabine and tenofovir disoproxil fumarate. Closely monitor hepatic function with both clinical and laboratory follow-up for at least several months in patients who are coinfected with HIV-1 and HBV and discontinue efavirenz, emtricitabine and tenofovir disoproxil fumarate. If appropriate, initiation of anti-hepatitis B therapy may be warranted. (5.1)

1 INDICATIONS AND USAGE

Efavirenz, emtricitabine and tenofovir disoproxil fumarate tablet is a three-drug combination of efavirenz (EFV), a non-nucleoside reverse transcriptase inhibitor, and emtricitabine (FTC) and tenofovir disoproxil fumarate (TDF), both HIV-1 nucleoside analog reverse transcriptase inhibitors, and is indicated as a complete regimen or in combination with other antiretroviral agents for the treatment of HIV-1 infection in adults and pediatric patients weighing at least 40 kg. (1)

2 DOSAGE AND ADMINISTRATION

- Testing: Consult Full Prescribing Information for important testing recommendations prior to initiation and during treatment with efavirenz, emtricitabine and tenofovir disoproxil fumarate tablets. (2.1)
- Recommended dosage in adults and pediatric patients weighing at least 40 kg: One tablet once daily taken orally on an empty stomach, preferably at bedtime. (2.2)
- Renal impairment: Not recommended in patients with estimated creatinine clearance below 50 mL/min. (2.3)
- Hepatic impairment: Not recommended in patients with moderate to severe hepatic impairment. (2.4)
- Dosage adjustment with rifampin coadministration: An additional 200 mg/day of efavirenz is recommended for patients weighing 50 kg or more. (2.5)

3 DOSAGE FORMS AND STRENGTHS

Tablets: 600 mg of efavirenz, 200 mg of emtricitabine, and 300 mg of tenofovir disoproxil fumarate. (3)

4 CONTRAINDICATIONS

- Previously demonstrated hypersensitivity (e.g., Stevens-Johnson syndrome, erythema multiforme, or toxic skin eruptions) to efavirenz, a component of efavirenz, emtricitabine and tenofovir disoproxil fumarate tablets. (4)
- Coadministration with voriconazole. (4)
- Coadministration with elbasvir/grazoprevir. (4)

5 WARNINGS AND PRECAUTIONS

- Rash: Discontinue if severe rash develops. (5.2, 6.1)
- Hepatotoxicity: Monitor liver function tests before and during treatment in patients with underlying hepatic disease, including hepatitis B or C coinfection, marked transaminase elevations, or who are taking medications associated with liver toxicity. Among reported cases of hepatic failure, a few occurred in patients with no pre-existing hepatic disease. (5.3, 6.2, 8.7)
- Risk of adverse reactions or loss of virologic response due to drug interactions: Consult full prescribing information prior to and during treatment for important potential drug interactions. Consider alternatives to efavirenz, emtricitabine and tenofovir disoproxil fumarate in patients taking other medications with a known risk of Torsade de Pointes or in patients at higher risk of Torsade de Pointes. (5.4)
- Serious psychiatric symptoms: Immediate medical evaluation is recommended. (5.5, 6.1)
- Nervous system symptoms (NSS): NSS are frequent, usually begin 1 to 2 days after initiating therapy, and resolve in 2 to 4 weeks. Dosing at bedtime may improve tolerability. NSS are not predictive of onset of psychiatric symptoms. (2.2, 5.6)
- New onset or worsening renal impairment: Can include acute renal failure and Fanconi syndrome. Prior to initiation and during use of efavirenz, emtricitabine and tenofovir disoproxil fumarate, assess serum creatinine, estimated creatinine clearance, urine glucose, and urine protein in all patients. In patients with chronic kidney disease, also assess serum phosphorus. Avoid administering efavirenz, emtricitabine and tenofovir disoproxil fumarate with concurrent or recent use of nephrotoxic drugs. (5.7)
- Embryo fetal toxicity: Fetal harm may occur when administered to a pregnant woman during the first trimester. Avoid pregnancy while receiving efavirenz, emtricitabine and tenofovir disoproxil fumarate and for 12 weeks after discontinuation. (5.8, 8.1)
- Decreases in bone mineral density (BMD): Consider assessment of BMD in patients with a history of pathological fracture or other risk factors for osteoporosis or bone loss. (5.9)
- Convulsions: Use caution in patients with a history of seizures. (5.10)
- Lactic acidosis/severe hepatomegaly with steatosis: Discontinue treatment in patients who develop symptoms or laboratory findings suggestive of lactic acidosis or pronounced hepatotoxicity. (5.11)
- Immune reconstitution syndrome: May necessitate further evaluation and treatment. (5.12)
- Redistribution/accumulation of body fat: Observed in patients receiving antiretroviral therapy. (5.13)

6 ADVERSE REACTIONS

Most common adverse reactions (incidence greater than or equal to 10%) observed in an active-controlled clinical trial of EFV, FTC, and TDF are diarrhea, nausea, fatigue, headache, dizziness, depression, insomnia, abnormal dreams, and rash. (6.1)

To report SUSPECTED ADVERSE REACTIONS, contact Aurobindo Pharma USA, Inc. at 1-866-850-2876 or FDA at 1-800-FDA-1088 or www.fda.gov/medwatch.

7 DRUG INTERACTIONS

- Consult Full Prescribing Information prior to and during treatment for important potential drug interactions. (4, 5.4, 7)
- HIV-1 protease inhibitors: Coadministration of efavirenz, emtricitabine and tenofovir disoproxil fumarate with either lopinavir/ritonavir or darunavir and ritonavir increases tenofovir concentrations. Monitor for evidence of tenofovir toxicity. Coadministration ofefavirenz, emtricitabine and tenofovir disoproxil fumaratewith either atazanavir or atazanavir and ritonavir is not recommended. (7.3)

8 USE IN SPECIFIC POPULATIONS

- Pregnancy: Avoid pregnancy while receiving efavirenz, emtricitabine and tenofovir disoproxil fumarate and for 12 weeks after discontinuation. (5.8, 8.3)
- Lactation: Breastfeeding is not recommended. (8.2)
- Females and Males of Reproductive Potential: Pregnancy testing and contraception are recommended. (8.3)
- Pediatrics: The incidence of rash was higher than in adults. (5.2, 6.1)

FULL PRESCRIBING INFORMATION

WARNING: POSTTREATMENT ACUTE EXACERBATION OF HEPATITIS B

Severe acute exacerbations of hepatitis B virus (HBV) have been reported in patients who are coinfected with HIV-1 and HBV and have discontinued products containing emtricitabine (FTC) and/or tenofovir disoproxil fumarate (TDF), which are components of efavirenz, emtricitabine and tenofovir disoproxil fumarate.
Closely monitor hepatic function with both clinical and laboratory follow-up for at least several months in patients who are coinfected with HIV-1 and HBV and discontinue efavirenz, emtricitabine and tenofovir disoproxil fumarate. If appropriate, initiation of anti-hepatitis B therapy may be warranted [see Warnings and Precautions (5.1)].

1 INDICATIONS AND USAGE

Efavirenz, emtricitabine and tenofovir disoproxil fumarate tabletsare indicated as a complete regimen or in combination with other antiretroviral agents for the treatment of HIV-1 infection in adults and pediatric patients weighing at least 40 kg.

2 DOSAGE AND ADMINISTRATION

2.1 Testing Prior to Initiation and During Treatment with Efavirenz, Emtricitabine and Tenofovir Disoproxil Fumarate Tablets

Prior to or when initiating efavirenz, emtricitabine and tenofovir disoproxil fumarate tablets, test patients for hepatitis B virus infection [see Warnings and Precautions (5.1)].
Prior to initiation and during use of efavirenz, emtricitabine and tenofovir disoproxil fumarate tablets, on a clinically appropriate schedule, assess serum creatinine, estimated creatinine clearance, urine glucose and urine protein in all patients. In patients with chronic kidney disease, also assess serum phosphorus [see Warnings and Precautions (5.7)].
Monitor hepatic function prior to and during treatment with efavirenz, emtricitabine and tenofovir disoproxil fumarate tablets [see Warnings and Precautions (5.3)].
Perform pregnancy testing before initiation of efavirenz, emtricitabine and tenofovir disoproxil fumarate tablets are in adolescents and adults of childbearing potential [see Warnings and Precautions (5.8), Use in Specific Populations (8.1, 8.3)].

2.2 Recommended Dosage for Adults and Pediatric Patients Weighing at Least 40 kg

Efavirenz, emtricitabine and tenofovir disoproxil fumarate tablet is a three-drug fixed-dose combination product containing 600 mg of efavirenz (EFV), 200 mg of emtricitabine (FTC), and 300 mg of tenofovir disoproxil fumarate (TDF). The recommended dosage of efavirenz, emtricitabine and tenofovir disoproxil fumarate tablets in adults and pediatric patients weighing at least 40 kg is one tablet once daily taken orally on an empty stomach. Dosing at bedtime may improve the tolerability of nervous system symptoms [see Clinical Pharmacology (12.3)].

2.3 Not Recommended in Patients with Moderate or Severe Renal Impairment

Efavirenz, emtricitabine and tenofovir disoproxil fumarate tablets are not recommended in patients with moderate or severe renal impairment (estimated creatinine clearance below 50 mL/min) [see Warnings and Precautions (5.7), Use in Specific Populations (8.6)].

2.4 Not Recommended in Patients with Moderate to Severe Hepatic Impairment

Efavirenz, emtricitabine and tenofovir disoproxil fumarate tablets are not recommended in patients with moderate to severe hepatic impairment (Child-Pugh B or C) [see Warnings and Precautions (5.3) and Use in Specific Populations (8.7)].

2.5 Dosage Adjustment with Rifampin

If efavirenz, emtricitabine and tenofovir disoproxil fumarate tablets areco-administered with rifampin in patients weighing 50 kg or more, take one tablet of efavirenz, emtricitabine and tenofovir disoproxil fumarate once daily followed by one additional 200 mg per day of efavirenz [see Drug Interactions (7.3) and Clinical Pharmacology (12.3)].

3 DOSAGE FORMS AND STRENGTHS

Efavirenz, emtricitabine and tenofovir disoproxil fumarate tablets are white to off-white, oval shaped, biconvex, film-coated tablets debossed with “I48” on one side and plain on the other side. Each tablet contains 600 mg of efavirenz, 200 mg of emtricitabine, and 300 mg of tenofovir disoproxil fumarate (equivalent to 245 mg of tenofovir disoproxil).

4 CONTRAINDICATIONS

- Efavirenz, emtricitabine and tenofovir disoproxil fumarate tablets are contraindicated in patients with previously demonstrated clinically significant hypersensitivity (e.g., Stevens-Johnson syndrome, erythema multiforme, or toxic skin eruptions) to efavirenz, a component of efavirenz, emtricitabine and tenofovir disoproxil fumarate tablets [see Warnings and Precautions (5.2)].
- Efavirenz, emtricitabine and tenofovir disoproxil fumarate tablets are contraindicated to be coadministered with voriconazole or elbasvir/grazoprevir [see Drug Interactions (7.3) and Clinical Pharmacology (12.3)].

5 WARNINGS AND PRECAUTIONS

5.1 Severe Acute Exacerbation of Hepatitis B in Patients Coinfected with HIV-1 and HBV

All patients should be tested for the presence of chronic HBV before or when initiating antiretroviral therapy [see Dosage and Administration (2.1)]. Severe acute exacerbations of hepatitis B (e.g., liver decompensation and liver failure) have been reported in patients who are coinfected with HBV and HIV-1 and have discontinued FTC or TDF, two of the components of efavirenz, emtricitabine and tenofovir disoproxil fumarate. Patients who are coinfected with HIV-1 and HBV should be closely monitored, with both clinical and laboratory follow-up for at least several months after stopping treatment with efavirenz, emtricitabine and tenofovir disoproxil fumarate. If appropriate, initiation of anti-hepatitis B therapy may be warranted, especially in patients with advanced liver disease or cirrhosis, since posttreatment exacerbation of hepatitis may lead to hepatic decompensation and liver failure.

5.2 Rash

In controlled clinical trials, 26% (266/1,008) of adult subjects treated with 600 mg EFV experienced new-onset skin rash compared with 17% (111/635) of those treated in control groups. Rash associated with blistering, moist desquamation, or ulceration occurred in 0.9% (9/1,008) of subjects treated with EFV. The incidence of Grade 4 rash (e.g., erythema multiforme, Stevens-Johnson syndrome) in adult subjects treated with EFV in all trials and expanded access was 0.1%. Rashes are usually mild-to-moderate maculopapular skin eruptions that occur within the first 2 weeks of initiating therapy with EFV (median time to onset of rash in adults was 11 days) and, in most subjects continuing therapy with EFV, rash resolves within 1 month (median duration, 16 days). The discontinuation rate for rash in adult clinical trials was 1.7% (17/1,008). Efavirenz, emtricitabine and tenofovir disoproxil fumaratecan be reinitiated in patients interrupting therapy because of rash. Efavirenz, emtricitabine and tenofovir disoproxil fumarateshould be discontinued in patients developing severe rash associated with blistering, desquamation, mucosal involvement, or fever. Appropriate antihistamines and/or corticosteroids may improve the tolerability and hasten the resolution of rash. For patients who have had a life-threatening cutaneous reaction (e.g., Stevens-Johnson syndrome), alternative therapy should be considered [see Contraindications (4)].

Experience with EFV in subjects who discontinued other antiretroviral agents of the NNRTI class is limited. Nineteen subjects who discontinued nevirapine because of rash have been treated with EFV. Nine of these subjects developed mild-to-moderate rash while receiving therapy with EFV, and two of these subjects discontinued because of rash.

Rash was reported in 59 of 182 pediatric subjects (32%) treated with EFV [see Adverse Reactions (6.1)]. Two pediatric subjects experienced Grade 3 rash (confluent rash with fever, generalized rash), and four subjects had Grade 4 rash (erythema multiforme). The median time to onset of rash in pediatric subjects was 28 days (range 3 to 1,642 days). Prophylaxis with appropriate antihistamines before initiating therapy with efavirenz, emtricitabine and tenofovir disoproxil fumarate in pediatric patients should be considered.

5.3 Hepatotoxicity

Postmarketing cases of hepatitis, including fulminant hepatitis progressing to liver failure requiring transplantation or resulting in death, have been reported in patients treated with EFV, a component of efavirenz, emtricitabine and tenofovir disoproxil fumarate. Reports have included patients with underlying hepatic disease, including coinfection with hepatitis B or C, and patients without pre-existing hepatic disease or other identifiable risk factors [see Warnings and Precautions (5.1)].
Efavirenz, emtricitabine and tenofovir disoproxil fumarate is not recommended for patients with moderate or severe hepatic impairment. Careful monitoring is recommended for patients with mild hepatic impairment receiving efavirenz, emtricitabine and tenofovir disoproxil fumarate [see Adverse Reactions (6.2) and Use in Specific Populations (8.7)].
Monitoring of liver enzymes before and during treatment is recommended for all patients [see Dosage and Administration (2.1)]. Consider discontinuing efavirenz, emtricitabine and tenofovir disoproxil fumarate in patients with persistent elevations of serum transaminases to greater than five times the upper limit of the normal range.
Discontinue efavirenz, emtricitabine and tenofovir disoproxil fumarate if elevation of serum transaminases is accompanied by clinical signs or symptoms of hepatitis or hepatic decompensation [see Adverse Reactions (6.1)].

5.4 Risk of Adverse Reactions or Loss of Virologic Response Due to Drug Interactions

The concomitant use of efavirenz, emtricitabine and tenofovir disoproxil fumarate and other drugs may result in potentially significant drug interactions [see Contraindications (4) and Drug Interactions (7.3)], some of which may lead to:

- Loss of therapeutic effect of concomitant drug or efavirenz, emtricitabine and tenofovir disoproxil fumarate and possible development of resistance.
- Possible clinically significant adverse reaction from greater exposures of efavirenz, emtricitabine and tenofovir disoproxil fumarate or concomitant drug.

QTc prolongation has been observed with the use of EFV [see Drug Interactions (7.1) and Clinical Pharmacology (12.2)]. Consider alternatives to efavirenz, emtricitabine and tenofovir disoproxil fumarate when coadministered with a drug with a known risk of Torsade de Pointes or when administered to patients at higher risk of Torsade de Pointes.

See Table 3 for steps to prevent or manage these possible and known significant drug interactions, including dosing recommendations. Consider the potential for drug interactions prior to and during efavirenz, emtricitabine and tenofovir disoproxil fumarate therapy and review concomitant medications during efavirenz, emtricitabine and tenofovir disoproxil fumarate therapy [see Dosage and Administration (2.5), Contraindications (4), and Drug Interactions (7)].

5.5 Psychiatric Symptoms

Serious psychiatric adverse experiences have been reported in patients treated with EFV, a component of efavirenz, emtricitabine and tenofovir disoproxil fumarate. In controlled trials of 1,008 subjects treated with regimens containing EFV for a mean of 2.1 years and 635 subjects treated with control regimens for a mean of 1.5 years, the frequency (regardless of causality) of specific serious psychiatric events among subjects who received EFV or control regimens, respectively, were: severe depression (2.4%, 0.9%), suicidal ideation (0.7%, 0.3%), nonfatal suicide attempts (0.5%, 0%), aggressive behavior (0.4%, 0.5%), paranoid reactions (0.4%, 0.3%), and manic reactions (0.2%, 0.3%). When psychiatric symptoms similar to those noted above were combined and evaluated as a group in a multifactorial analysis of data from Study AI266006 (006, NCT00002410), a Phase 3 randomized, open-label trial of EFV-containing regimens versus controls in 1,266 subjects (median follow-up 180 weeks, 102 weeks, and 76 weeks for subjects treated with EFV + zidovudine + lamivudine, EFV + indinavir, and indinavir + zidovudine + lamivudine, respectively), treatment with EFV was associated with an increase in the occurrence of these selected psychiatric symptoms. Other factors associated with an increase in the occurrence of these psychiatric symptoms were history of injection drug use, psychiatric history, and receipt of psychiatric medication at trial entry; similar associations were observed in both the EFV and control treatment groups. In Study 006, onset of new serious psychiatric symptoms occurred throughout the trial for both EFV-treated and control-treated subjects. One percent of EFV-treated subjects discontinued or interrupted treatment because of one or more of these selected psychiatric symptoms. There have also been occasional postmarketing reports of death by suicide, delusions, and psychosis-like behavior, although a causal relationship to the use of EFV cannot be determined from these reports. Postmarketing cases of catatonia have also been reported and may be associated with increased EFV exposure. Patients with serious psychiatric adverse experiences should seek immediate medical evaluation to assess the possibility that the symptoms may be related to the use of EFV, and if so, to determine whether the risks of continued therapy outweigh the benefits [see Adverse Reactions (6)].

5.6 Nervous System Symptoms

Fifty-three percent (531/1,008) of subjects receiving EFV in controlled trials reported central nervous system symptoms (any grade, regardless of causality) compared to 25% (156/635) of subjects receiving control regimens. These symptoms included dizziness (28.1% of the 1,008 subjects), insomnia (16.3%), impaired concentration (8.3%), somnolence (7.0%), abnormal dreams (6.2%), and hallucinations (1.2%). Other reported symptoms were euphoria, confusion, agitation, amnesia, stupor, abnormal thinking, and depersonalization. The majority of these symptoms were mild to moderate (50.7%); symptoms were severe in 2.0% of subjects. Overall, 2.1% of subjects discontinued therapy as a result. These symptoms usually begin during the first or second day of therapy and generally resolve after the first 2 to 4 weeks of therapy. After 4 weeks of therapy, the prevalence of nervous system symptoms of at least moderate severity ranged from 5% to 9% in subjects treated with regimens containing EFV and from 3% to 5% in subjects treated with a control regimen. Patients should be informed that these common symptoms were likely to improve with continued therapy and were not predictive of subsequent onset of the less frequent psychiatric symptoms [see Warnings and Precautions (5.5)]. Dosing at bedtime may improve the tolerability of these nervous system symptoms [see Dosage and Administration (2.2)].

Analysis of long-term data from Study 006 showed that, beyond 24 weeks of therapy, the incidences of new-onset nervous system symptoms among EFV-treated subjects were generally similar to those in the indinavir-containing control arm.

Late-onset neurotoxicity, including ataxia and encephalopathy (impaired consciousness, confusion, psychomotor slowing, psychosis, delirium), may occur months to years after beginning EFV therapy. Some events of late-onset neurotoxicity have occurred in patients with CYP2B6 genetic polymorphisms which are associated with increased EFV levels despite standard dosing of EFV. Patients presenting with signs and symptoms of serious neurologic adverse experiences should be evaluated promptly to assess the possibility that these events may be related to EFV use, and whether discontinuation of efavirenz, emtricitabine and tenofovir disoproxil fumarate is warranted.

Patients receiving efavirenz, emtricitabine and tenofovir disoproxil fumarateshould be alerted to the potential for additive central nervous system effects when efavirenz, emtricitabine and tenofovir disoproxil fumarate is used concomitantly with alcohol or psychoactive drugs.

Patients who experience central nervous system symptoms such as dizziness, impaired concentration, and/or drowsiness should avoid potentially hazardous tasks such as driving or operating machinery.

5.7 New Onset or Worsening Renal Impairment

Emtricitabine and tenofovir are principally eliminated by the kidney; however, EFV is not. Renal impairment, including cases of acute renal failure and Fanconi syndrome (renal tubular injury with severe hypophosphatemia), has been reported with the use of TDF, a component of efavirenz emtricitabine and tenofovir disoproxil fumarate [see Adverse Reactions (6.2)].

Prior to initiation and during use of efavirenz, emtricitabine and tenofovir disoproxil fumarate, on a clinically appropriate schedule, assess serum creatinine, estimated creatinine clearance, urine glucose, and urine protein in all patients. In patients with chronic kidney disease, also assess serum phosphorus. Efavirenz, emtricitabine and tenofovir disoproxil fumarate is not recommended in patients with moderate or severe renal impairment (estimated creatinine clearance below 50 mL/min).

Efavirenz, emtricitabine and tenofovir disoproxil fumarate should be avoided with concurrent or recent use of a nephrotoxic agent (e.g., high-dose or multiple non-steroidal anti-inflammatory drugs [NSAIDs]) [see Drug Interactions (7.2)]. Cases of acute renal failure after initiation of high-dose or multiple NSAIDs have been reported in HIV-infected patients with risk factors for renal dysfunction who appeared stable on TDF. Some patients required hospitalization and renal replacement therapy. Alternatives to NSAIDs should be considered, if needed, in patients at risk for renal dysfunction.

Persistent or worsening bone pain, pain in extremities, fractures, and/or muscular pain or weakness may be manifestations of proximal renal tubulopathy and should prompt an evaluation of renal function in patients at risk of renal dysfunction.

Discontinue efavirenz, emtricitabine and tenofovir disoproxil fumarate in patients who develop clinically significant decreases in renal function or evidence of Fanconi syndrome.

5.8 Embryo-Fetal Toxicity

Efavirenz may cause fetal harm when administered during the first trimester of pregnancy. Advise adults and adolescents of childbearing potential who are receiving efavirenz, emtricitabine and tenofovir disoproxil fumarate to avoid pregnancy while receiving efavirenz, emtricitabine and tenofovir disoproxil fumarate and for 12 weeks after discontinuation [see Dosage and Administration (2.1), Use in Specific Populations (8.1, 8.3)].

5.9 Bone Loss and Mineralization Defects

Bone Mineral Density

In clinical trials in HIV-1 infected adults, TDF (a component of efavirenz, emtricitabine and tenofovir disoproxil fumarate) was associated with slightly greater decreases in bone mineral density (BMD) and increases in biochemical markers of bone metabolism, suggesting increased bone turnover relative to comparators. Serum parathyroid hormone levels and 1,25 Vitamin D levels were also higher in subjects receiving TDF.

Clinical trials evaluating TDF in pediatric and adolescent subjects were conducted. Under normal circumstances, BMD increases rapidly in pediatric patients. In HIV-1 infected subjects aged 2 years to less than 18 years, bone effects were similar to those observed in adult subjects and suggest increased bone turnover. Total body BMD gain was less in the TDF-treated HIV-1 infected pediatric subjects as compared to the control groups. Similar trends were observed in chronic hepatitis-B infected adolescent subjects aged 12 years to less than 18 years. In all pediatric trials, skeletal growth (height) appeared to be unaffected.

The effects of TDF-associated changes in BMD and biochemical markers on long-term bone health and future fracture risk are unknown. Assessment of BMD should be considered for adult and pediatric patients who have a history of pathologic bone fracture or other risk factors for osteoporosis or bone loss. Although the effect of supplementation with calcium and vitamin D was not studied, such supplementation may be beneficial for all patients. If bone abnormalities are suspected, then appropriate consultation should be obtained.

Mineralization Defects

Cases of osteomalacia associated with proximal renal tubulopathy, manifested as bone pain or pain in extremities and which may contribute to fractures, have been reported in association with TDF use [see Adverse Reactions (6.2)]. Arthralgias and muscle pain or weakness have also been reported in cases of proximal renal tubulopathy. Hypophosphatemia and osteomalacia secondary to proximal renal tubulopathy should be considered in patients at risk of renal dysfunction who present with persistent or worsening bone or muscle symptoms while receiving TDF-containing products [see Warnings and Precautions (5.7)].

5.10 Convulsions

Convulsions have been observed in adult and pediatric patients receiving EFV, generally in the presence of known medical history of seizures. Caution must be taken in any patient with a history of seizures.

Patients who are receiving concomitant anticonvulsant medications primarily metabolized by the liver, such as phenytoin and phenobarbital, may require periodic monitoring of plasma levels [see Drug Interactions (7.3)].

5.11 Lactic Acidosis/Severe Hepatomegaly with Steatosis

Lactic acidosis and severe hepatomegaly with steatosis, including fatal cases, have been reported with the use of nucleoside analogs, including TDF and FTC, components of efavirenz, emtricitabine and tenofovir disoproxil fumarate, alone or in combination with other antiretrovirals. Treatment with efavirenz, emtricitabine and tenofovir disoproxil fumarate should be suspended in any patient who develops clinical or laboratory findings suggestive of lactic acidosis or pronounced hepatotoxicity (which may include hepatomegaly and steatosis even in the absence of marked transaminase elevations).

5.12 Immune Reconstitution Syndrome

Immune reconstitution syndrome has been reported in patients treated with combination antiretroviral therapy, including the components of efavirenz, emtricitabine and tenofovir disoproxil fumarate. During the initial phase of combination antiretroviral treatment, patients whose immune system responds may develop an inflammatory response to indolent or residual opportunistic infections (such as Mycobacterium avium infection, cytomegalovirus, Pneumocystis jirovecii pneumonia [PCP], or tuberculosis), which may necessitate further evaluation and treatment.

Autoimmune disorders (such as Graves’ disease, polymyositis, Guillain-Barré syndrome, and autoimmune hepatitis) have also been reported to occur in the setting of immune reconstitution; however, the time to onset is more variable, and can occur many months after initiation of treatment.

5.13 Fat Redistribution

Redistribution/accumulation of body fat, including central obesity, dorsocervical fat enlargement (buffalo hump), peripheral wasting, facial wasting, breast enlargement, and “cushingoid appearance,” has been observed in patients receiving antiretroviral therapy, including EFV. The mechanism and long-term consequences of these events are currently unknown. A causal relationship has not been established.

6 ADVERSE REACTIONS

The following adverse reactions are discussed in other sections of the labeling:

- Severe Acute Exacerbations of Hepatitis B in Patients Coinfected with HIV-1 and HBV [see Warnings and Precautions (5.1)].
- Rash [see Warnings and Precautions (5.2)].
- Hepatotoxicity [see Warnings and Precautions (5.3)].
- Psychiatric Symptoms [see Warnings and Precautions (5.5)].
- Nervous System Symptoms [see Warnings and Precautions (5.6)].
- New Onset or Worsening Renal Impairment [see Warnings and Precautions (5.7)].
- Embryo-Fetal Toxicity [see Warnings and Precautions (5.8)].
- Bone Loss and Mineralization Defects [see Warnings and Precautions (5.9)].
- Convulsions [see Warnings and Precautions (5.10)].
- Lactic Acidosis/Severe Hepatomegaly with Steatosis [see Warnings and Precautions (5.11)].
- Immune Reconstitution Syndrome [see Warnings and Precautions (5.12)].
- Fat Redistribution [see Warnings and Precautions (5.13)].

6.1 Clinical Trials Experience

Because clinical trials are conducted under widely varying conditions, adverse reaction rates observed in the clinical trials of a drug cannot be directly compared to rates in the clinical trials of another drug and may not reflect the rates observed in practice.

Clinical Trials in Adult Subjects

Study 934 was an open-label active-controlled trial in which 511 antiretroviral-naïve subjects received either FTC + TDF administered in combination with EFV (N=257) or zidovudine (AZT)/lamivudine (3TC) administered in combination with EFV (N=254).

The most common adverse reactions (incidence greater than or equal to 10%, any severity) occurring in Study 934 include diarrhea, nausea, fatigue, headache, dizziness, depression, insomnia, abnormal dreams, and rash. Adverse reactions observed in Study 934 were generally consistent with those seen in previous trials of the individual components (Table 1).

Table 1 Selected Adverse Reactionsa (Grades 2 to 4) Reported in ≥5% in Either Treatment Group in Study 934 (0 to 144 Weeks)

 | FTC+TDF+EFVb | AZT/3TC+EFV
 | N=257 | N=254
Fatigue | 9% | 8%
Depression | 9% | 7%
Nausea | 9% | 7%
Diarrhea | 9% | 5%
Dizziness | 8% | 7%
Upper respiratory tract infections | 8% | 5%
Sinusitis | 8% | 4%
Rash Eventc | 7% | 9%
Headache | 6% | 5%
Insomnia | 5% | 7%
Anxiety | 5% | 4%
Nasopharyngitis | 5% | 3%
Vomiting | 2% | 5%

a. Frequencies of adverse reactions are based on all treatment-emergent adverse events, regardless of relationship to study drug.

b. From Weeks 96 to 144 of the trial, subjects received FTC/TDF administered in combination with EFV in place of FTC + TDF with EFV.

c. Rash event includes rash, exfoliative rash, rash generalized, rash macular, rash maculopapular, rash pruritic, and rash vesicular.

In Study 073, subjects with stable, virologic suppression on antiretroviral therapy and no history of virologic failure were randomized to receive efavirenz, emtricitabine and tenofovir disoproxil fumarate or to stay on their baseline regimen. The adverse reactions observed in Study 073 were generally consistent with those seen in Study 934 and those seen with the individual components of efavirenz, emtricitabine and tenofovir disoproxil fumarate when each was administered in combination with other antiretroviral agents.

Efavirenz, Emtricitabine, or TDF

In addition to the adverse reactions in Study 934 and Study 073, the following adverse reactions were observed in clinical trials of EFV, FTC, or TDF in combination with other antiretroviral agents.

Efavirenz: The most significant adverse reactions observed in subjects treated with EFV were nervous system symptoms [see Warnings and Precautions (5.6)], psychiatric symptoms [see Warnings and Precautions (5.5)], and rash [see Warnings and Precautions (5.2)].

Selected adverse reactions of moderate-to-severe intensity observed in greater than or equal to 2% of EFV-treated subjects in two controlled clinical trials included pain, impaired concentration, abnormal dreams, somnolence, anorexia, dyspepsia, abdominal pain, nervousness, and pruritus.

Pancreatitis has also been reported, although a causal relationship with EFV has not been established. Asymptomatic increases in serum amylase levels were observed in a significantly higher number of subjects treated with EFV 600 mg than in control subjects.

Skin discoloration has been reported with higher frequency among FTC-treated subjects; it was manifested by hyperpigmentation on the palms and/or soles and was generally mild and asymptomatic. The mechanism and clinical significance are unknown.

Clinical Trials in Pediatric Subjects

Efavirenz: Assessment of adverse reactions is based on three pediatric clinical trials in 182 HIV-1 infected pediatric subjects who received EFV in combination with other antiretroviral agents for a median of 123 weeks. The type and frequency of adverse reactions in the three trials were generally similar to that of adult subjects with the exception of a higher incidence of rash, which was reported in 32% (59/182) of pediatric subjects compared to 26% of adults, and a higher frequency of Grade 3 or 4 rash reported in 3% (6/182) of pediatric subjects compared to 0.9% of adults [see Warnings and Precautions (5.2)].

Emtricitabine: In addition to the adverse reactions reported in adults, anemia and hyperpigmentation were observed in 7% and 32%, respectively, of pediatric subjects who received treatment with FTC in the larger of two open-label, uncontrolled pediatric trials (N=116).

Tenofovir DF: In a pediatric clinical trial conducted in subjects 12 to less than 18 years of age, the adverse reactions observed in pediatric subjects who received treatment with TDF (N=81) were consistent with those observed in clinical trials of TDF in adults [see Warnings and Precautions (5.9)].

Laboratory Abnormalities

Efavirenz, Emtricitabine and Tenofovir DF: Laboratory abnormalities observed in Study 934 were generally consistent with those seen in previous trials (Table 2).

Table 2 Significant Laboratory Abnormalities Reported in ≥1% of Subjects in Either Treatment Group in Study 934 (0 to 144 Weeks)

 | FTC+TDF+EFVa | AZT/3TC+EFV
 | N=257 | N=254
Any ≥ Grade 3 Laboratory Abnormality | 30% | 26%
Fasting Cholesterol (>240 mg/dL) | 22% | 24%
Creatine Kinase (M: >990 U/L) (F: >845 U/L) | 9% | 7%
Serum Amylase (>175 U/L) | 8% | 4%
Alkaline Phosphatase (>550 U/L) | 1% | 0%
AST (M: >180 U/L) (F: >170 U/L) | 3% | 3%
ALT (M: >215 U/L) (F: >170 U/L) | 2% | 3%
Hemoglobin (<8.0 mg/dL) | 0% | 4%
Hyperglycemia (>250 mg/dL) | 2% | 1%
Hematuria (>75 RBC/HPF) | 3% | 2%
Glycosuria (≥3+) | <1% | 1%
Neutrophils (<750/mm^3) | 3% | 5%
Fasting Triglycerides (>750 mg/dL) | 4% | 2%

a. From Weeks 96 to 144 of the trial, subjects received FTC/TDF administered in combination with EFV in place of FTC + TDF with EFV.

Laboratory abnormalities observed in Study 073 were generally consistent with those in Study 934.

Hepatic Events: In Study 934, 19 subjects treated with EFV, FTC, and TDF and 20 subjects treated with EFV and fixed-dose zidovudine/lamivudine were hepatitis B surface antigen or hepatitis C antibody positive. Among these coinfected subjects, one subject (1/19) in the EFV, FTC, and TDF arm had elevations in transaminases to greater than five times ULN through 144 weeks. In the fixed-dose zidovudine/lamivudine arm, two subjects (2/20) had elevations in transaminases to greater than five times ULN through 144 weeks. No HBV and/or HCV coinfected subject discontinued from the trial due to hepatobiliary disorders [see Warnings and Precautions (5.3)].

6.2 Postmarketing Experience

The following adverse reactions have been identified during postapproval use of EFV, FTC, or TDF. Because postmarketing reactions are reported voluntarily from a population of uncertain size, it is not always possible to reliably estimate their frequency or establish a causal relationship to drug exposure.

Efavirenz:

Cardiac Disorders
Palpitations

Ear and Labyrinth Disorders
Tinnitus, vertigo

Endocrine Disorders
Gynecomastia

Eye Disorders
Abnormal vision

Gastrointestinal Disorders
Constipation, malabsorption

General Disorders and Administration Site Conditions
Asthenia

Hepatobiliary Disorders
Hepatic enzyme increase, hepatic failure, hepatitis

Immune System Disorders
Allergic reactions

Metabolism and Nutrition Disorders
Redistribution/accumulation of body fat [see Warnings and Precautions (5.13)], hypercholesterolemia, hypertriglyceridemia

Musculoskeletal and Connective Tissue Disorders
Arthralgia, myalgia, myopathy

Nervous System Disorders
Abnormal coordination, ataxia, encephalopathy, cerebellar coordination and balance disturbances, convulsions, hypoesthesia, paresthesia, neuropathy, tremor

Psychiatric Disorders
Aggressive reactions, agitation, delusions, emotional lability, mania, neurosis, paranoia, psychosis, suicide, catatonia

Respiratory, Thoracic and Mediastinal Disorders
Dyspnea

Skin and Subcutaneous Tissue Disorders
Flushing, erythema multiforme, photoallergic dermatitis, Stevens-Johnson syndrome

Emtricitabine: No postmarketing adverse reactions have been identified for inclusion in this section.

Tenofovir DF:

Immune System Disorders
Allergic reaction, including angioedema

Metabolism and Nutrition Disorders
Lactic acidosis, hypokalemia, hypophosphatemia

Respiratory, Thoracic, and Mediastinal Disorders
Dyspnea

Gastrointestinal Disorders
Pancreatitis, increased amylase, abdominal pain

Hepatobiliary Disorders
Hepatic steatosis, hepatitis, increased liver enzymes (most commonly AST, ALT, gamma GT)

Skin and Subcutaneous Tissue Disorders
Rash

Musculoskeletal and Connective Tissue Disorders
Rhabdomyolysis, osteomalacia (manifested as bone pain and which may contribute to fractures), muscular weakness, myopathy

Renal and Urinary Disorders
Acute renal failure, renal failure, acute tubular necrosis, Fanconi syndrome, proximal renal tubulopathy, interstitial nephritis (including acute cases), nephrogenic diabetes insipidus, renal insufficiency, increased creatinine, proteinuria, polyuria

General Disorders and Administration Site Conditions
Asthenia

The following adverse reactions, listed under the body system headings above, may occur as a consequence of proximal renal tubulopathy: rhabdomyolysis, osteomalacia, hypokalemia, muscular weakness, myopathy, hypophosphatemia.

7 DRUG INTERACTIONS

7.1 Efavirenz

Efavirenz has been shown in vivo to induce CYP3A and CYP2B6. Other compounds that are substrates of CYP3A or CYP2B6 may have decreased plasma concentrations when coadministered with EFV.

Drugs that induce CYP3A activity (e.g., phenobarbital, rifampin, rifabutin) would be expected to increase the clearance of EFV, resulting in lowered plasma concentrations [see Dosage and Administration (2.2)].

There is limited information available on the potential for a pharmacodynamic interaction between EFV and drugs that prolong the QTc interval. QTc prolongation has been observed with the use of EFV [see Clinical Pharmacology (12.2)]. Consider alternatives to efavirenz emtricitabine and tenofovir disoproxil fumarate when coadministered with a drug with a known risk of Torsade de Pointes.

7.2 Drugs Affecting Renal Function

FTC and tenofovir are primarily eliminated by the kidneys [see Clinical Pharmacology (12.3)]. Coadministration of efavirenz, emtricitabine and tenofovir disoproxil fumarate with drugs that are eliminated by active tubular secretion may increase concentrations of FTC, tenofovir, and/or the coadministered drug. Some examples include, but are not limited to, acyclovir, adefovir dipivoxil, cidofovir, ganciclovir, valacyclovir, valganciclovir, aminoglycosides (e.g., gentamicin), and high-dose or multiple NSAIDs [see Warnings and Precautions (5.7)]. Drugs that decrease renal function may increase concentrations of FTC and/or tenofovir.

7.3 Established and Potentially Significant Interactions

Other important drug interaction information for efavirenz, emtricitabine and tenofovir disoproxil fumarateis summarized in Table 3. The drug interactions described are based on trials conducted with either efavirenz, emtricitabine and tenofovir disoproxil fumarate, the components of efavirenz, emtricitabine and tenofovir disoproxil fumarate (EFV, FTC, or TDF) as individual agents, or are potential drug interactions [see Clinical Pharmacology (12.3)].

Table 3 Established and Potentially Significanta Drug Interactions
Concomitant Drug Class: Drug Name | Effect |  | Clinical Comment
HIV antiviral agents
Protease inhibitor: atazanavir | ↓ atazanavir ↑ tenofovir |  | Coadministration of atazanavir with efavirenz, emtricitabine and tenofovir disoproxil fumarate is not recommended. The combined effect of EFV plus TDF on atazanavir plasma concentrations is not known. There are insufficient data to support dosing recommendations for atazanavir or atazanavir/ritonavir in combination with efavirenz, emtricitabine and tenofovir disoproxil fumarate.
Protease inhibitor: fosamprenavir calcium | ↓ amprenavir |  | Fosamprenavir (unboosted): Appropriate doses of fosamprenavir and efavirenz, emtricitabine and tenofovir disoproxil fumarate with respect to safety and efficacy have not been established. Fosamprenavir/ritonavir: An additional 100 mg/day (300 mg total) of ritonavir is recommended when efavirenz, emtricitabine and tenofovir disoproxil fumarate is administered with fosamprenavir/ritonavir once daily. No change in the ritonavir dose is required when efavirenz, emtricitabine and tenofovir disoproxil fumarate is administered with fosamprenavir plus ritonavir twice daily.
Protease inhibitor: indinavir | ↓ indinavir |  | The optimal dose of indinavir, when given in combination with EFV, is not known. Increasing the indinavir dose to 1000 mg every 8 hours does not compensate for the increased indinavir metabolism due to EFV.
Protease inhibitor: darunavir/ritonavir lopinavir/ritonavir | ↑ tenofovir ↓ lopinavir ↑ tenofovir |  | Monitor patients receiving efavirenz, emtricitabine and tenofovir disoproxil fumarate concomitantly with ritonavir-boosted darunavir for TDF-associated adverse reactions. Discontinue efavirenz, emtricitabine and tenofovir disoproxil fumarate in patients who develop TDF-associated adverse reactions. Do not use once daily administration of lopinavir/ritonavir. Dose increase of lopinavir/ritonavir is recommended for all patients when coadministered with EFV. Refer to the Full Prescribing Information for lopinavir/ritonavir for guidance on coadministration with EFV- or tenofovir-containing regimens, such as efavirenz, emtricitabine and tenofovir disoproxil fumarate. Patients should be monitored for tenofovir-associated adverse reactions. Discontinue efavirenz, emtricitabine and tenofovir disoproxil fumarate in patients who develop TDF-associated adverse reactions.
Protease inhibitor: ritonavir | ↑ ritonavir ↑ efavirenz |  | When ritonavir 500 mg every 12 hours was coadministered with EFV 600 mg once daily, the combination was associated with a higher frequency of adverse clinical experiences (e.g., dizziness, nausea, paresthesia) and laboratory abnormalities (elevated liver enzymes). Monitoring of liver enzymes is recommended when efavirenz, emtricitabine and tenofovir disoproxil fumarate is used in combination with ritonavir.
Protease inhibitor: saquinavir | ↓ saquinavir |  | Appropriate doses of the combination of EFV and saquinavir/ritonavir with respect to safety and efficacy have not been established.
CCR5 co-receptor antagonist: maraviroc | ↓ maraviroc |  | Refer to the full prescribing information for maraviroc for guidance on coadministration with efavirenz, emtricitabine and tenofovir disoproxil fumarate.
NRTI: didanosine | ↑ didanosine |  | Patients receiving efavirenz, emtricitabine and tenofovir disoproxil fumarate and didanosine should be monitored closely for didanosine-associated adverse reactions. Discontinue didanosine in patients who develop didanosine-associated adverse reactions. Higher didanosine concentrations could potentiate didanosine- associated adverse reactions, including pancreatitis, and neuropathy. Suppression of CD4+ cell counts has been observed in patients receiving TDF with didanosine 400 mg daily. In patients weighing greater than 60 kg, reduce the didanosine dose to 250 mg when it is coadministered with efavirenz, emtricitabine and tenofovir disoproxil fumarate. In patients weighing less than 60 kg, reduce the didanosine dose to 200 mg when it is coadministered with efavirenz, emtricitabine and tenofovir disoproxil fumarate tablets. When coadministered, efavirenz, emtricitabine and tenofovir disoproxil fumarate and Videx EC may be taken under fasted conditions or with a light meal (less than 400 kcal, 20% fat).
NNRTI: Other NNRTIs | ↑ or ↓ efavirenz and/or NNRTI |  | Combining two NNRTIs has not been shown to be beneficial. Efavirenz, emtricitabine and tenofovir disoproxil fumarate contains EFV and should not be coadministered with other NNRTIs.
Integrase strand transfer inhibitor: raltegravir | ↓ raltegravir |  | The clinical significance of this interaction has not been directly assessed.
Hepatitis C antiviral agents
boceprevir | ↓ boceprevir |  | Plasma trough concentrations of boceprevir were decreased when boceprevir was coadministered with EFV, which may result in loss of therapeutic effect. The combination should be avoided.
elbasvir/grazoprevir | ↓ elbasvir ↓ grazoprevir |  | Coadministration of efavirenz, emtricitabine and tenofovir disoproxil fumarate with elbasvir/grazoprevir is contraindicated [see Contraindications (4)] because it may lead to loss of virologic response to elbasvir/grazoprevir.
glecaprevir/pibrentasvir | ↓ glecaprevir ↓ pibrentasvir |  | Coadministration of efavirenz, emtricitabine and tenofovir disoproxil fumarate is not recommended because it may lead to reduced therapeutic effect of glecaprevir/pibrentasvir.
ledipasvir/sofosbuvir | ↑ tenofovir |  | Patients receiving efavirenz, emtricitabine and tenofovir disoproxil fumarate and HARVONI® (ledipasvir/sofosbuvir) concomitantly should be monitored for adverse reactions associated with TDF.
simeprevir | ↓ simeprevir ↔ efavirenz |  | Concomitant administration of simeprevir with EFV is not recommended because it may result in loss of therapeutic effect of simeprevir.
sofosbuvir/velpatasvir sofosbuvir/velpatasvir/ voxilaprevir | ↑ tenofovir ↓ velpatasvir ↓ voxilaprevir |  | Coadministration of EFV-containing regimens and EPCLUSA® (sofosbuvir/velpatasvir) or VOSEVI® (sofosbuvir/velpatasvir/voxilaprevir) is not recommended.
Other agents
Anticoagulant: warfarin | ↑ or ↓ warfarin |  | Plasma concentrations and effects potentially increased or decreased by EFV.
Anticonvulsants: carbamazepine | ↓ carbamazepine ↓ efavirenz |  | There are insufficient data to make a dose recommendation for efavirenz, emtricitabine and tenofovir disoproxil fumarate. Alternative anticonvulsant treatment should be used.
phenytoin phenobarbital | ↓ anticonvulsant ↓ efavirenz |  | Potential for reduction in anticonvulsant and/or EFV plasma levels; periodic monitoring of anticonvulsant plasma levels should be conducted.
Antidepressants: bupropion | ↓ bupropion |  | The effect of EFV on bupropion exposure is thought to be due to the induction of bupropion metabolism. Increases in bupropion dosage should be guided by clinical response, but the maximum recommended dose of bupropion should not be exceeded.
sertraline | ↓ sertraline |  | Increases in sertraline dose should be guided by clinical response.
Antifungals: itraconazole | ↓ itraconazole ↓ hydroxy- itraconazole |  | Since no dose recommendation for itraconazole can be made, alternative antifungal treatment should be considered.
ketoconazole | ↓ ketoconazole |  | Drug interaction trials with efavirenz, emtricitabine and tenofovir disoproxil fumarate and ketoconazole have not been conducted. Efavirenz has the potential to decrease plasma concentrations of ketoconazole.
posaconazole | ↓ posaconazole |  | Avoid concomitant use unless the benefit outweighs the risks.
voriconazole | ↓ voriconazole ↑ efavirenz |  | Coadministration of efavirenz, emtricitabine and tenofovir disoproxil fumarate with voriconazole is contraindicated [see Contraindications (4)] because it may lead to reduced therapeutic effect of voriconazole and increased risk of EFV-associated adverse reactions
Anti-infective: clarithromycin | ↓ clarithromycin ↑ 14-OH metabolite |  | Consider alternatives to macrolide antibiotics because of the risk of QT interval prolongation.
Antimycobacterial: rifabutin | ↓ rifabutin |  | Increase daily dose of rifabutin by 50%. Consider doubling the rifabutin dose in regimens where rifabutin is given 2 or 3 times a week.
rifampin | ↓ efavirenz |  | If efavirenz, emtricitabine and tenofovir disoproxil fumarate is coadministered with rifampin to patients weighing 50 kg or more, an additional 200 mg/day of EFV is recommended.
Antimalarials: artemether/ lumefantrine atovaquone/proguanil | ↓ artemether ↓ dihydroartemisinin ↓ lumefantrine ↓ atovaquone ↓ proguanil |  | Consider alternatives to artemether/lumefantrine because of the risk of QT interval prolongation [see Warnings and Precautions (5.4)]. Concomitant administration of atovaquone/proguanil with efavirenz, emtricitabine and tenofovir disoproxil fumarate is not recommended.
Calcium channel blockers: diltiazem | ↓ diltiazem ↓ desacetyl diltiazem ↓ N-monodes-methyl diltiazem |  | Diltiazem dose adjustments should be guided by clinical response (refer to the full prescribing information for diltiazem). No dose adjustment of efavirenz, emtricitabine and tenofovir disoproxil fumarate is necessary when administered with diltiazem.
Others e.g., felodipine nicardipine nifedipine verapamil | ↓ calcium channel blocker |  | No data are available on the potential interactions of EFV with other calcium channel blockers that are substrates of CYP3A. The potential exists for reduction in plasma concentrations of the calcium channel blocker. Dose adjustments should be guided by clinical response (refer to the full prescribing information for the calcium channel blocker).
HMG-CoA reductase inhibitors: atorvastatin pravastatin simvastatin | ↓ atorvastatin ↓ pravastatin ↓ simvastatin |  | Plasma concentrations of atorvastatin, pravastatin, and simvastatin decreased with EFV. Consult the Full Prescribing Information for the HMG-CoA reductase inhibitor for guidance on individualizing the dose.
Hormonal contraceptives: Oral: ethinyl estradiol/norgestimate Implant: etonogestrel | ↓ active metabolites of norgestimate ↓ etonogestrel |  | A reliable method of barrier contraception must be used in addition to hormonal contraceptives. Efavirenz had no effect on ethinyl estradiol concentrations, but progestin levels (norelgestromin and levonorgestrel) were markedly decreased. No effect of ethinyl estradiol/norgestimate on EFV plasma concentrations was observed. A reliable method of barrier contraception must be used in addition to hormonal contraceptives. Decreased exposure of etonogestrel may be expected. There have been postmarketing reports of contraceptive failure with etonogestrel in EFV- exposed patients.
Immunosuppressants: cyclosporine, tacrolimus, sirolimus, and others metabolized by CYP3A | ↓ immuno- suppressant |  | Decreased exposure of the immunosuppressant may be expected due to CYP3A induction by EFV. These immunosuppressants are not anticipated to affect exposure of EFV. Dose adjustments of the immunosuppressant may be required. Close monitoring of immunosuppressant concentrations for at least 2 weeks (until stable concentrations are reached) is recommended when starting or stopping treatment with efavirenz, emtricitabine and tenofovir disoproxil fumarate.
Narcotic analgesic: methadone | ↓ methadone |  | Coadministration of EFV in HIV-1 infected individuals with a history of injection drug use resulted in signs of opiate withdrawal. Methadone dose was increased by a mean of 22% to alleviate withdrawal symptoms. Patients should be monitored for signs of withdrawal and their methadone dose increased as required to alleviate withdrawal symptoms.
a. This table is not all inclusive.

7.4 Efavirenz Assay Interference

Cannabinoid Test Interaction: Efavirenz does not bind to cannabinoid receptors. False-positive urine cannabinoid test results have been reported with some screening assays in uninfected and HIV-infected subjects receiving EFV. Confirmation of positive screening tests for cannabinoids by a more specific method is recommended.

8 USE IN SPECIFIC POPULATIONS

8.1 Pregnancy

Antiretroviral Pregnancy Registry

There is a pregnancy exposure registry that monitors pregnancy outcomes in adults and adolescents exposed to efavirenz, emtricitabine and tenofovir disoproxil fumarate during pregnancy. Healthcare providers are encouraged to register patients by calling the Antiretroviral Pregnancy Registry (APR) at (800) 258-4263.

Risk Summary

There are retrospective case reports of neural tube defects in infants whose mothers were exposed to EFV-containing regimens in the first trimester of pregnancy. Prospective pregnancy data from the APR are not sufficient to adequately assess this risk. Although a causal relationship has not been established between exposure to EFV in the first trimester and neural tube defects, similar malformations have been observed in studies conducted in monkeys at doses similar to the human dose (see Data). In addition, fetal and embryonic toxicities occurred in rats at a dose 10 times less than the human exposure at the recommended clinical human dose (RHD) of EFV. Because of the potential risk of neural tube defects, EFV is not recommended for use in the first trimester of pregnancy. Avoid pregnancy while receiving efavirenz, emtricitabine and tenofovir disoproxil fumarate and for 12 weeks after discontinuation. Advise pregnant patients of the potential risk to a fetus.

Available data from the APR show no increase in the overall risk of major birth defects for EFV, FTC, or TDF compared with the background rate for major birth defects of 2.7% in a U.S. reference population of the Metropolitan Atlanta Congenital Defects Program (MACDP) (see Data).

The rate of miscarriage is not reported in the APR. The estimated background rate of miscarriage in clinically recognized pregnancies in the U.S. general population is 15 to 20%. The background risk of major birth defects and miscarriage for the indicated population is unknown. The APR uses the MACDP as the U.S. reference population for birth defects in the general population. The MACDP evaluates mothers and infants from a limited geographic area and does not include outcomes for births that occurred at less than 20 weeks’ gestation.

In animal reproduction studies, no adverse developmental effects were observed when FTC and TDF were administered separately at doses/exposures ≥60 (FTC), ≥14 (TDF) and 2.7 (tenofovir) times those at the RHD of efavirenz, emtricitabine and tenofovir disoproxil fumarate (see Data).

Data

Human Data

Efavirenz: There are retrospective postmarketing reports of findings consistent with neural tube defects, including meningomyelocele, all in infants of mothers exposed to EFV-containing regimens in the first trimester.

Based on prospective reports to the APR of 1,217 exposures to EFV-containing regimens during pregnancy resulting in live births (including over 1,023 live births exposed in the first trimester and 194 exposed in the second/third trimester), there was no increase in overall birth defects with EFV compared with the background birth defect rate of 2.7% in the U.S. reference population of the MACDP. The prevalence of birth defects in live births was 2.3% (95% CI: 1.5% to 3.5%) with first trimester exposure to EFV-containing regimens, and 1.5% (95% CI: 0.3% to 4.5%) with the second/third trimester exposure to EFV-containing regimens. One of these prospectively reported defects with first-trimester exposure was a neural tube defect. A single case of anophthalmia with first-trimester exposure to EFV has also been prospectively reported. This case also included severe oblique facial clefts and amniotic banding, which have a known association with anophthalmia.

Emtricitabine: Based on prospective reports from the APR of 4,005 exposures to FTC-containing regimens during pregnancy resulting in live births (including 2,785 exposed in the first trimester and 1,220 exposed in the second/third trimester), there was no increase in overall major birth defects with FTC compared with the background birth defect rate of 2.7% in the U.S. reference population of the MACDP. The prevalence of birth defects in live births was 2.4% (95% CI: 1.9% to 3.1%) with first trimester exposure to FTC-containing regimens and 2.3% (95% CI: 1.5% to 3.3%) with the second/third trimester exposure to FTC-containing regimens.

Tenofovir DF: Based on prospective reports from the APR of 5,105 exposures to TDF-containing regimens during pregnancy resulting in live births (including 3,535 exposed in the first trimester and 1,570 exposed in the second/third trimester), there was no increase in overall major birth defects with TDF compared with the background birth defect rate of 2.7% in the U.S. reference population of the MACDP. The prevalence of birth defects in live births was 2.3% (95% CI: 1.8% to 2.9%) with first trimester exposure to TDF-containing regimens, and 2.2% (95% CI: 1.6% to 3.1%) with the second/third trimester exposure to TDF-containing regimens.

Animal Data

Efavirenz: Effects of EFV on embryo-fetal development have been studied in three nonclinical species (cynomolgus monkeys, rats, and rabbits). In monkeys, EFV 60 mg/kg/day was administered to pregnant females throughout pregnancy (gestation Days 20 through 150). The maternal systemic drug exposures (AUC) were 1.3 times the exposures at the RHD, with fetal umbilical venous drug concentrations approximately 0.7 times the maternal values. Three fetuses of 20 fetuses/infants had one or more malformations; there were no malformed fetuses or infants from placebo-treated mothers. The malformations that occurred in these three monkey fetuses included anencephaly and unilateral anophthalmia in one fetus, microphthalmia in a second, and cleft palate in the third. There was no NOAEL (no observable adverse effect level) established for this study because only one dosage was evaluated. In rats, EFV was administered either during organogenesis (gestation Days 7 to 18) or from gestation Day 7 through lactation Day 21 at 50, 100, or 200 mg/kg/day. Administration of 200 mg/kg/day in rats was associated with an increase in the incidence of early resorptions, and doses 100 mg/kg/day and greater were associated with early neonatal mortality. The AUC at the NOAEL (50 mg/kg/day) in this rat study was 0.1 times that in humans at the RHD. Drug concentrations in the milk on lactation Day 10 were approximately 8 times higher than those in maternal plasma. In pregnant rabbits, EFV was neither embryo lethal nor teratogenic when administered at doses of 25, 50, and 75 mg/kg/day over the period of organogenesis (gestation Days 6 through 18). The AUC at the NOAEL (75 mg/kg/day) in rabbits was 0.4 times that in humans at the RHD.

Emtricitabine: FTC was administered orally to pregnant mice (at 0, 250, 500, or 1,000 mg/kg/day), and rabbits (at 0, 100, 300, or 1,000 mg/kg/day) through organogenesis (on gestation days 6 through 15, and 7 through 19, respectively). No significant toxicological effects were observed in embryo-fetal toxicity studies performed with FTC in mice at exposures (AUC) approximately 60 times higher and in rabbits at approximately 120 times higher than human exposures at the RHD. In a pre/postnatal development study in mice, FTC was administered orally at doses up to 1000 mg/kg/day; no significant adverse effects directly related to drug were observed in the offspring exposed daily from before birth (in utero) through sexual maturity at daily exposures (AUC) of approximately 60 times higher than human exposures at the RHD.

Tenofovir DF: TDF was administered orally to pregnant rats (at 0, 50, 150, or 450 mg/kg/day) and rabbits (at 0, 30, 100, or 300 mg/kg/day) through organogenesis (on gestation days 7 through 17, and 6 through 18, respectively). No significant toxicological effects were observed in embryo-fetal toxicity studies performed with TDF in rats at doses up to 14 times the RHD based on body surface area comparisons and in rabbits at doses up to 19 times the RHD based on body surface area comparisons. In a pre/postnatal development study in rats, TDF was administered orally through lactation at doses up to 600 mg/kg/day; no adverse effects were observed in the offspring at tenofovir exposures of approximately 2.7 times higher than human exposures at the RHD.

8.2 Lactation

Risk Summary

The Centers for Disease Control and Prevention recommend that HIV-1 infected mothers not breastfeed their infants to avoid risking postnatal transmission of HIV-1.

Based on limited published data, EFV, FTC, and tenofovir have been shown to be present in human breast milk.

It is not known if the components of efavirenz, emtricitabine and tenofovir disoproxil fumarate affect milk production or have effects on the breastfed child. Because of the potential for: (1) HIV transmission (in HIV-negative infants); (2) developing viral resistance (in HIV-positive infants); and (3) adverse reactions in a breastfed infant similar to those seen in adults, instruct mothers not to breastfeed if they are receiving efavirenz, emtricitabine and tenofovir disoproxil fumarate.

8.3 Females and Males of Reproductive Potential

Pregnancy Testing

Perform pregnancy testing in adults and adolescents of childbearing potential before initiation of efavirenz, emtricitabine and tenofovir disoproxil fumarate because of potential risk of neural tube defects [see Use in Specific Populations (8.1)].

Contraception

Advise adults and adolescents of childbearing potential to use effective contraception during treatment with efavirenz, emtricitabine and tenofovir disoproxil fumarate and for 12 weeks after discontinuing efavirenz, emtricitabine and tenofovir disoproxil fumarate due to the long half-life of EFV, a component of efavirenz, emtricitabine and tenofovir disoproxil fumarate. Hormonal methods that contain progesterone may have decreased effectiveness Always use barrier contraception in combination with other methods of contraception [see Drug Interactions (7.1, 7.3)].

8.4 Pediatric Use

The effectiveness and safety of efavirenz, emtricitabine and tenofovir disoproxil fumarate as a complete regimen for the treatment of HIV-1 infection was established in pediatric patients with body weight greater than or equal to 40 kg [see Dosage and Administration (2.2)]. Use of efavirenz, emtricitabine and tenofovir disoproxil fumarate in this age group is supported by adequate and well-controlled studies of efavirenz, emtricitabine and tenofovir disoproxil fumarate in adults with HIV-1 infection and data from pediatric studies of the individual components of efavirenz, emtricitabine and tenofovir disoproxil fumarate (EFV, FTC, and TDF).

Efavirenz, emtricitabine and tenofovir disoproxil fumarate should only be administered to pediatric patients with a body weight greater than or equal to 40 kg. Because efavirenz, emtricitabine and tenofovir disoproxil fumarate is a fixed-dose combination tablet, the dose of efavirenz, emtricitabine and tenofovir disoproxil fumarate cannot be adjusted for patients of lower weight [see Warnings and Precautions (5.2, 5.9), Adverse Reactions (6.1), and Clinical Pharmacology (12.3)].

8.5 Geriatric Use

Clinical trials of EFV, FTC, or TDF did not include sufficient numbers of subjects aged 65 and over to determine whether they respond differently from younger subjects. In general, dose selection for elderly patients should be cautious, keeping in mind the greater frequency of decreased hepatic, renal, or cardiac function, and of concomitant disease or other drug therapy.

8.6 Renal Impairment

Because efavirenz, emtricitabine and tenofovir disoproxil fumarate is a fixed-dose combination, and cannot be dose adjusted, it is not recommended in patients with moderate or severe renal impairment (estimated creatinine clearance below 50 mL/min) [see Dosage and Administration (2.3), Warnings and Precautions (5.7)].

8.7 Hepatic Impairment

Efavirenz, emtricitabine and tenofovir disoproxil fumarate is not recommended for patients with moderate or severe hepatic impairment because there are insufficient data to determine an appropriate dose. Patients with mild hepatic impairment may be treated with efavirenz, emtricitabine and tenofovir disoproxil fumarate at the approved dose. Because of the extensive cytochrome P450-mediated metabolism of EFV and limited clinical experience in patients with hepatic impairment, caution should be exercised in administering efavirenz, emtricitabine and tenofovir disoproxil fumarate to these patients [see Dosage and Administration (2.4), Warnings and Precautions (5.3), and Clinical Pharmacology (12.3)].

10 OVERDOSAGE

If overdose occurs, the patient should be monitored for evidence of toxicity, and standard supportive treatment applied as necessary. Administration of activated charcoal may be used to aid removal of unabsorbed EFV. Hemodialysis can remove both FTC and TDF (refer to detailed information below) but is unlikely to significantly remove EFV from the blood.

Efavirenz: Some patients accidentally taking 600 mg twice daily have reported increased nervous system symptoms. One patient experienced involuntary muscle contractions.

Emtricitabine: Hemodialysis treatment removes approximately 30% of the FTC dose over a 3-hour dialysis period starting within 1.5 hours of FTC dosing (blood flow rate of 400 mL/min and a dialysate flow rate of 600 mL/min). It is not known whether FTC can be removed by peritoneal dialysis.

Tenofovir DF: Tenofovir is efficiently removed by hemodialysis with an extraction coefficient of approximately 54%. Following a single 300 mg dose of TDF, a 4-hour hemodialysis session removed approximately 10% of the administered tenofovir dose.

11 DESCRIPTION

Efavirenz, emtricitabine and tenofovir disoproxil fumarateis a fixed-dose combination tablet containing EFV, FTC, and TDF. EFV is a non-nucleoside reverse transcriptase inhibitor (NNRTI). FTC is a synthetic nucleoside analog of cytidine. TDF, which is converted in vivo to tenofovir, is an acyclic nucleoside phosphonate (nucleotide) analog of adenosine 5′-monophosphate.

Efavirenz, emtricitabine and tenofovir disoproxil fumaratetablets are for oral administration. Each tablet contains 600 mg of EFV, 200 mg of FTC, and 300 mg of TDF (equivalent to 245 mg of tenofovir disoproxil) as active ingredients. The tablets include the following inactive ingredients: croscarmellose sodium, hydroxypropyl cellulose, magnesium stearate, microcrystalline cellulose, and sodium lauryl sulfate. The tablets are film-coated with a coating material containing polyethylene glycol, polyvinyl alcohol, talc, and titanium dioxide.

Efavirenz: EFV is chemically described as (S)-6-chloro-4-(cyclopropylethynyl)-1,4-dihydro-4-(trifluoromethyl)-2H-3,1-benzoxazin-2-one. Its molecular formula is C14H9ClF3NO2 and its structural formula is:

Efavirenz USP is a white to off-white, crystalline powder with a molecular mass of 315.68. It is practically insoluble in water (less than 10 mcg/mL).

Emtricitabine: The chemical name of FTC is 5-fluoro-1-(2R,5S)-[2-(hydroxymethyl)-1,3-oxathiolan-5-yl]cytosine. FTC is the (-) enantiomer of a thio analog of cytidine, which differs from other cytidine analogs in that it has a fluorine in the 5-position.

It has a molecular formula of C8H10FN3O3S and a molecular weight of 247.24. It has the following structural formula:

Emtricitabine is a white to off-white powder with a solubility of approximately 112 mg/mL in water at 25ºC.

Tenofovir DF: TDF is a fumaric acid salt of the bis-isopropoxycarbonyloxymethyl ester derivative of tenofovir. The chemical name of TDF is 9-[(R)-2[[bis[[(isopropoxycarbonyl)oxy]-methoxy]phosphinyl]methoxy]propyl]adenine fumarate (1:1). It has a molecular formula of C19H30N5O10P • C4H4O4 and a molecular weight of 635.52. It has the following structural formula:
TDF is a white to off-white crystalline powder with a solubility of 13.4 mg/mL in water at 25°C.

12 CLINICAL PHARMACOLOGY

12.1 Mechanism of Action

Efavirenz, emtricitabine and tenofovir disoproxil fumarate is a fixed-dose combination of antiviral drugs EFV, FTC, and TDF [see Microbiology (12.4)].

12.2 Pharmacodynamics

Cardiac Electrophysiology

Efavirenz: The effect of EFV on the QTc interval was evaluated in an open-label, positive and placebo-controlled, fixed single sequence 3-period, 3-treatment crossover QT study in 58 healthy subjects enriched for CYP2B6 polymorphisms. The mean Cmax of EFV in subjects with CYP2B6 *6/*6 genotype following the administration of 600 mg daily dose for 14 days was 2.25-fold the mean Cmax observed in subjects with CYP2B6 *1/*1 genotype. A positive relationship between EFV concentration and QTc prolongation was observed. Based on the concentration-QTc relationship, the mean QTc prolongation and its upper bound 90% confidence interval are 8.7 msec and 11.3 msec in subjects with CYP2B6*6/*6 genotype following the administration of 600 mg daily dose for 14 days [see Warnings and Precautions (5.4)].

12.3 Pharmacokinetics

Efavirenz, Emtricitabine and Tenofovir Disoproxil Fumarate: One efavirenz, emtricitabine and tenofovir disoproxil fumarate tablet is bioequivalent to one Sustiva tablet (600 mg) plus one EMTRIVA® capsule (200 mg) plus one VIREAD® tablet (300 mg) following single-dose administration to fasting healthy subjects (N=45).

Efavirenz: In HIV-1 infected subjects time-to-peak plasma concentrations were approximately 3 to 5 hours and steady-state plasma concentrations were reached in 6 to 10 days. In 35 HIV-1 infected subjects receiving EFV 600 mg once daily, steady-state Cmax was 12.9 ± 3.7 µM (mean ± SD), Cmin was 5.6 ± 3.2 µM, and AUC was 184 ± 73 µM•hr. EFV is highly bound (approximately 99.5 to 99.75%) to human plasma proteins, predominantly albumin. Following administration of ^14C-labeled EFV, 14 to 34% of the dose was recovered in the urine (mostly as metabolites) and 16 to 61% was recovered in feces (mostly as parent drug). In vitro studies suggest CYP3A and CYP2B6 are the major isozymes responsible for EFV metabolism. EFV has been shown to induce CYP enzymes, resulting in induction of its own metabolism. EFV has a terminal half-life of 52 to 76 hours after single doses and 40 to 55 hours after multiple doses.

Emtricitabine: Following oral administration, FTC is rapidly absorbed, with peak plasma concentrations occurring at 1 to 2 hours postdose. Following multiple dose oral administration of FTC to 20 HIV-1 infected subjects, the steady-state plasma FTC Cmax was 1.8 ± 0.7 mcg/mL (mean ± SD) and the AUC over a 24-hour dosing interval was 10.0 ± 3.1 mcg•hr/mL. The mean steady-state plasma trough concentration at 24 hours postdose was 0.09 mcg/mL. The mean absolute bioavailability of FTC was 93%. Less than 4% of FTC binds to human plasma proteins in vitro, and the binding is independent of concentration over the range of 0.02 to 200 mcg/mL. Following administration of radiolabelled FTC, approximately 86% is recovered in the urine and 13% is recovered as metabolites. The metabolites of FTC include 3′-sulfoxide diastereomers and their glucuronic acid conjugate. FTC is eliminated by a combination of glomerular filtration and active tubular secretion with a renal clearance in adults with normal renal function of 213 ± 89 mL/min (mean ± SD). Following a single oral dose, the plasma FTC half-life is approximately 10 hours.

Tenofovir DF: Following oral administration of a single 300 mg dose of TDF to HIV-1 infected subjects in the fasted state, maximum serum concentrations (Cmax) were achieved in 1.0 ± 0.4 hrs (mean ± SD) and Cmax and AUC values were 296 ± 90 ng/mL and 2287 ± 685 ng•hr/mL, respectively. The oral bioavailability of tenofovir from TDF in fasted subjects is approximately 25%. Less than 0.7% of tenofovir binds to human plasma proteins in vitro, and the binding is independent of concentration over the range of 0.01 to 25 mcg/mL. Approximately 70 to 80% of the intravenous dose of tenofovir is recovered as unchanged drug in the urine. Tenofovir is eliminated by a combination of glomerular filtration and active tubular secretion, with a renal clearance in adults with normal renal function of 243 ± 33 mL/min (mean ± SD). Following a single oral dose, the terminal elimination half-life of tenofovir is approximately 17 hours.

Effects of Food on Oral Absorption

Efavirenz, emtricitabine and tenofovir disoproxil fumarate has not been evaluated in the presence of food. Administration of EFV tablets with a high-fat meal increased the mean AUC and Cmaxof EFV by 28% and 79%, respectively, compared to administration in the fasted state. Compared to fasted administration, dosing of TDF and FTC in combination with either a high-fat meal or a light meal increased the mean AUC and Cmax of tenofovir by 35% and 15%, respectively, without affecting FTC exposures [see Dosage and Administration (2.2) and Patient Counseling Information (17)].

Specific Populations

Race

Efavirenz: The pharmacokinetics of EFV in HIV-1 infected subjects appear to be similar among the racial groups studied.

Emtricitabine: No pharmacokinetic differences due to race have been identified following the administration of FTC.

Tenofovir DF: There were insufficient numbers from racial and ethnic groups other than Caucasian to adequately determine potential pharmacokinetic differences among these populations following the administration of TDF.

Gender

Efavirenz, Emtricitabine, and Tenofovir DF: EFV, FTC, and tenofovir pharmacokinetics are similar in male and female subjects.

Pediatric Patients

Efavirenz: In an open-label trial in NRTI-experienced pediatric subjects (mean age 8 years, range 3 to 16 years), the pharmacokinetics of EFV in pediatric subjects were similar to the pharmacokinetics in adults who received a 600 mg daily dose of EFV. Based on mean steady-state predicted population pharmacokinetic modeling in pediatric subjects weighing >40 kg receiving the 600 mg dose of EFV, Cmax was 6.57 mcg/mL, Cmin was 2.82 mcg/mL, and AUC(0-24) was 254.78 μM•hr.

Emtricitabine: The pharmacokinetics of FTC at steady state were determined in 27 HIV-1 infected pediatric subjects 13 to 17 years of age receiving a daily dose of 6 mg/kg up to a maximum dose of 240 mg oral solution or a 200 mg capsule; 26 of 27 subjects in this age group received the 200 mg capsule. Mean ± SD Cmax and AUC were 2.7 ± 0.9 mcg/mL and 12.6 ± 5.4 mcg•hr/mL, respectively. Exposures achieved in pediatric subjects 12 to less than 18 years of age were similar to those achieved in adults receiving a once daily dose of 200 mg.

Tenofovir DF: Steady-state pharmacokinetics of tenofovir were evaluated in 8 HIV-1 infected pediatric subjects (12 to less than 18 years). Mean ± SD Cmax and AUCtau are 0.38 ± 0.13 mcg/mL and 3.39 ± 1.22 mcg•hr/mL, respectively. Tenofovir exposure achieved in these pediatric subjects receiving oral daily doses of TDF 300 mg was similar to exposures achieved in adults receiving once-daily doses of TDF 300 mg.

Geriatric Patients
Pharmacokinetics of EFV, FTC, and tenofovir have not been fully evaluated in the elderly (65 years of age and older) [see Use in Specific Populations (8.5)].
Patients with Impaired Renal Function

Efavirenz: The pharmacokinetics of EFV have not been studied in subjects with renal insufficiency; however, less than 1% of EFV is excreted unchanged in the urine, so the impact of renal impairment on EFV elimination should be minimal.

Emtricitabine and Tenofovir DF: The pharmacokinetics of FTC and TDF are altered in subjects with renal impairment. In subjects with creatinine clearance below 50 mL/min, Cmax and AUC0-∞ of FTC and tenofovir were increased [see Warnings and Precautions (5.7)].

Patients with Hepatic Impairment

Efavirenz: A multiple-dose trial showed no significant effect on EFV pharmacokinetics in subjects with mild hepatic impairment (Child-Pugh Class A) compared with controls. There were insufficient data to determine whether moderate or severe hepatic impairment (Child-Pugh Class B or C) affects EFV pharmacokinetics [see Warnings and Precautions (5.3) and Use in Specific Populations (8.7)].

Emtricitabine: The pharmacokinetics of FTC have not been studied in subjects with hepatic impairment; however, FTC is not significantly metabolized by liver enzymes, so the impact of liver impairment should be limited.

Tenofovir DF: The pharmacokinetics of tenofovir following a 300 mg dose of TDF have been studied in non-HIV infected subjects with moderate to severe hepatic impairment. There were no substantial alterations in tenofovir pharmacokinetics in subjects with hepatic impairment compared with unimpaired subjects.

Assessment of Drug Interactions

The drug interaction trials described were conducted with either efavirenz, emtricitabine and tenofovir disoproxil fumarate or the components of efavirenz, emtricitabine and tenofovir disoproxil fumarate (EFV, FTC, or TDF) as individual agents.

Efavirenz: The steady-state pharmacokinetics of EFV and tenofovir were unaffected when EFV and TDF were administered together versus each agent dosed alone. Specific drug interaction trials have not been performed with EFV and NRTIs other than tenofovir, lamivudine, and zidovudine. Clinically significant interactions would not be expected based on NRTIs elimination pathways.

Efavirenz has been shown in vivo to cause hepatic enzyme induction, thus increasing the biotransformation of some drugs metabolized by CYP3A and CYP2B6. In vitro studies have shown that EFV inhibited CYP isozymes 2C9 and 2C19 with Ki values (8.5 to 17 µM) in the range of observed EFV plasma concentrations. In in vitro studies, EFV did not inhibit CYP2E1 and inhibited CYP2D6 and CYP1A2 (Ki values 82 to 160 µM) only at concentrations well above those achieved clinically. Coadministration of EFV with drugs primarily metabolized by CYP2C9, CYP2C19, CYP3A or CYP2B6 isozymes may result in altered plasma concentrations of the coadministered drug. Drugs which induce CYP3A and CYP2B6 activity would be expected to increase the clearance of EFV resulting in lowered plasma concentrations.

Drug interaction trials were performed with EFV and other drugs likely to be coadministered or drugs commonly used as probes for pharmacokinetic interaction. There was no clinically significant interaction observed between EFV and zidovudine, lamivudine, azithromycin, fluconazole, lorazepam, cetirizine, or paroxetine. Single doses of famotidine or an aluminum and magnesium antacid with simethicone had no effects on EFV exposures. The effects of coadministration of EFV on Cmax, AUC, and Cmin are summarized in Table 4 (effect of other drugs on EFV) and Table 5 (effect of EFV on other drugs) [see Drug Interactions (7)].

Table 4 Drug Interactions: Changes in Pharmacokinetic Parameters for EFV in the Presence of the Coadministered Drug
 |  |  |  | Mean % Change of EFV Pharmacokinetic Parametersa (90% CI)
Coadministered Drug | Dose of Coadministered Drug (mg) | EFV Dose (mg) | N | Cmax | AUC | Cmin
Lopinavir/ ritonavir | 400/100 mg q12h x 9 days | 600 mg qd x 9 days | 11, 12b | ↔ | ↓ 16 (↓ 38 to ↑ 15) | ↓ 16 (↓ 42 to ↑ 20)
Nelfinavir | 750 mg q8h x 7 days | 600 mg qd x 7 days | 10 | ↓ 12 (↓ 32 to ↑ 13)c | ↓ 12 (↓ 35 to ↑ 18)c | ↓ 21 (↓ 53 to ↑ 33)
Ritonavir | 500 mg q12h x 8 days | 600 mg qd x 10 days | 9 | ↑ 14 (↑ 4 to ↑ 26) | ↑ 21 (↑ 10 to ↑ 34) | ↑ 25 (↑ 7 to ↑ 46)c
Boceprevir | 800 mg tid x 6 days | 600 mg qd x 16 days | NA | ↑11 (↑ 2 to ↑ 20) | ↑ 20 (↑ 15 to ↑ 26) | NA
Rifabutin | 300 mg qd x 14 days | 600 mg qd x 14 days | 11 | ↔ | ↔ | ↓ 12 (↓ 24 to ↑ 1)
Rifampin | 600 mg x 7 days | 600 mg qd x 7 days | 12 | ↓ 20 (↓ 11 to ↓ 28) | ↓ 26 (↓ 15 to ↓ 36) | ↓ 32 (↓ 15 to ↓ 46)
Artemether/ lumefantrine | Artemether 20 mg/ lumefantrine 120 mg tablets (6 4-tablet doses over 3 days) | 600 mg qd × 26 days | 12 | ↔ | ↓17 | NA
Simvastatin | 40 mg qd × 4 days | 600 mg qd x 15 days | 14 | ↓ 12 (↓ 28 to ↑ 8) | ↔ | ↓ 12 (↓ 25 to ↑ 3)
Carbamazepine | 200 mg qd x 3 days, 200 mg bid x 3 days, then 400 mg qd x 15 days | 600 mg qd x 35 days | 14 | ↓ 21 (↓ 15 to ↓ 26) | ↓ 36 (↓ 32 to ↓ 40) | ↓ 47 (↓ 41 to ↓ 53)
Diltiazem | 240 mg x 14 days | 600 mg qd x 28 days | 12 | ↑ 16 (↑ 6 to ↑ 26) | ↑ 11 (↑ 5 to ↑ 18) | ↑ 13 (↑ 1 to ↑ 26)
Voriconazole | 400 mg po q12h x 1 day then 200 mg po q12h x 8 days | 400 mg qd x 9 days | NA | ↑ 38d | ↑ 44d | NA
Voriconazole | 300 mg po q12h days 2 to 7 | 300 mg qd x 7 days | NA | ↓ 14e (↓ 7 to ↓ 21) | ↔e | NA
Voriconazole | 400 mg po q12h days 2 to 7 | 300 mg qd x 7 days | NA | ↔e | ↑ 17e (↑ 6 to ↑ 29) | NA
NA = not available
a. Increase = ↑; Decrease = ↓; No Effect = ↔
b. Parallel-group design; N for EFV + lopinavir/ritonavir, N for EFV alone.
c. 95% CI
d. 90% CI not available
e. Relative to steady-state administration of EFV (600 mg once daily for 9 days).

No effect on the pharmacokinetic parameters of EFV was observed with the following coadministered drugs: indinavir, saquinavir soft gelatin capsule, simeprevir, ledipasvir/sofosbuvir, sofosbuvir, clarithromycin, itraconazole, atorvastatin, pravastatin, or sertraline.

Table 5 Drug Interactions: Changes in Pharmacokinetic Parameters for Coadministered Drug in the Presence of EFV
 |  |  |  | Mean % Change of Coadministered Drug Pharmacokinetic Parametersa (90% CI)
Coadministered Drug | Dose of Coadministered Drug (mg) | EFV Dose (mg) | N | Cmax | AUC | Cmin
Atazanavir | 400 mg qd with a light meal d 1 to 20 | 600 mg qd with a light meal d 7 to 20 | 27 | ↓ 59 (↓ 49 to ↓ 67) | ↓ 74 (↓ 68 to ↓ 78) | ↓ 93 (↓ 90 to ↓ 95)
Atazanavir | 400 mg qd d 1 to 6, then 300 mg qd d 7 to 20 with ritonavir 100 mg qd and a light meal | 600 mg qd 2 h after atazanavir and ritonavir d 7 to 20 | 13 | ↑ 14b (↓ 17 to ↑ 58) | ↑ 39b (↑ 2 to ↑ 88) | ↑ 48b (↑ 24 to ↑ 76)
Atazanavir | 300 mg qd/ritonavir 100 mg qd d 1 to 10 (pm), then 400 mg qd/ritonavir 100 mg qd d 11 to 24 (pm) (simultaneous with EFV) | 600 mg qd with a light snack d 11 to 24 (pm) | 14 | ↑ 17 (↑ 8 to ↑ 27) | ↔ | ↓ 42 (↓ 31 to ↓ 51)
Indinavir | 1000 mg q8h × 10 days | 600 mg qd × 10 days | 20
Indinavir | After morning dose |  |  | ↔c | ↓ 33c (↓ 26 to ↓ 39) | ↓ 39c (↓ 24 to ↓ 51)
Indinavir | After afternoon dose |  |  | ↔c | ↓ 37c (↓ 26 to ↓ 46) | ↓ 52c (↓ 47 to ↓ 57)
Indinavir | After evening dose |  |  | ↓ 29c (↓ 11 to ↓ 43) | ↓ 46c (↓ 37 to ↓ 54) | ↓ 57c (↓ 50 to ↓ 63)
Lopinavir/ ritonavir | 400/100 mg q12h x 9 days | 600 mg qd x 9 days | 11, 7d | ↔e | ↓ 19e (↓ 36 to ↑ 3) | ↓ 39e (↓ 3 to ↓ 62)
Nelfinavir Metabolite AG-1402 | 750 mg q8h x 7 days | 600 mg qd x 7 days | 10 | ↑ 21 (↑ 10 to ↑ 33) ↓ 40 (↓ 30 to ↓ 48) | ↑ 20 (↑ 8 to ↑ 34) ↓ 37 (↓ 25 to ↓ 48) | ↔ ↓ 43 (↓ 21 to ↓ 59)
Ritonavir | 500 mg q12h x 8 days | 600 mg qd x 10 days | 11
Ritonavir | After AM dose |  |  | ↑ 24 (↑ 12 to ↑ 38) | ↑ 18 (↑ 6 to ↑ 33) | ↑ 42 (↑ 9 to ↑ 86)f
Ritonavir | After PM dose |  |  | ↔ | ↔ | ↑ 24 (↑ 3 to ↑ 50)f
Saquinavir SGCg | 1200 mg q8h x 10 days | 600 mg qd x 10 days | 12 | ↓ 50 (↓ 28 to ↓ 66) | ↓ 62 (↓ 45 to ↓ 74) | ↓ 56 (↓ 16 to ↓ 77)f
Maraviroc | 100 mg bid | 600 mg qd | 12 | ↓ 51 (↓ 37 to ↓ 62) | ↓ 45 (↓ 38 to ↓ 51) | ↓ 45 (↓ 28 to ↓ 57)
Raltegravir | 400 mg single dose | 600 mg qd | 9 | ↓ 36 (↓ 2 to ↓ 59) | ↓ 36 (↓ 20 to ↓ 48) | ↓ 21 (↓ 51 to ↑ 28)
Boceprevir | 800 mg tid x 6 days | 600 mg qd x 16 days | NA | ↓ 8 (↓ 22 to ↑ 8) | ↓ 19 (↓ 11 to ↓ 25) | ↓ 44 (↓ 26 to ↓ 58)
Simeprevir | 150 mg qd × 14 days | 600 mg qd × 14 days | 23 | ↓ 51 (↓ 46 to ↓ 56) | ↓ 71 (↓ 67 to ↓ 74) | ↓ 91 (↓ 88 to ↓ 92)
Ledipasvir/ sofosbuvirk Ledipasvir Sofosbuvir GS-331007l | 90/400 mg qd x 14 days | 600 mg qd x 14 days | 15 | ↓ 34 (↓ 25 to ↓ 41) ↔ ↔ | ↓ 34 (↓ 25 to ↓ 41) ↔ ↔ | ↓ 34 (↓ 24 to ↓ 43) NA ↔
Sofosbuvirm GS-331007l | 400 mg qd single dose | 600 mg qd x 14 days | 16 | ↓ 19 (↓ 40 to ↑ 10) ↓ 23 (↓ 16 to ↓ 30) | ↔ ↓ 16 (↓ 24 to ↓ 8) | NA NA
Sofosbuvir/ velpatasvirn Sofosbuvir GS-331007l Velpatasvir | 400/100 mg qd × 14 days | 600 mg qd × 14 days | 14 | ↑ 38 (↑ 14 to ↑ 67) ↓ 14 (↓ 20 to ↓ 7) ↓ 47 (↓ 57 to ↓ 36) | ↔ ↔ ↓ 53 (↓ 61 to ↓ 43) | NA ↔ ↓ 57 (↓ 64 to ↓ 48)
Clarithromycin 14-OH metabolite | 500 mg q12h x 7 days | 400 mg qd x 7 days | 11 | ↓ 26 (↓ 15 to ↓ 35) ↑ 49 (↑ 32 to ↑ 69) | ↓ 39 (↓ 30 to ↓ 46) ↑ 34 (↑ 18 to ↑ 53) | ↓ 53 (↓ 42 to ↓ 63) ↑ 26 (↑ 9 to ↑ 45)
Itraconazole Hydroxy-itraconazole | 200 mg q12h x 28 days | 600 mg qd x 14 days | 18 | ↓ 37 (↓ 20 to ↓ 51) ↓ 35 (↓ 12 to ↓ 52) | ↓ 39 (↓ 21 to ↓ 53) ↓ 37 (↓ 14 to ↓ 55) | ↓ 44 (↓ 27 to ↓ 58) ↓ 43 (↓ 18 to ↓ 60)
Posaconazole | 400 mg (oral suspension) bid × 10 and 20 days | 400 mg qd × 10 and 20 days | 11 | ↓ 45 (↓ 34 to ↓ 53) | ↓ 50 (↓ 40 to ↓ 57) | NA
Rifabutin | 300 mg qd x 14 days | 600 mg qd x 14 days | 9 | ↓ 32 (↓ 15 to ↓ 46) | ↓ 38 (↓ 28 to ↓ 47) | ↓ 45 (↓ 31 to ↓ 56)
Artemether/ lumefantrine Artemether dihydroartemisinin lumefantrine | Artemether 20 mg/lumefantrine 120 mg tablets (6 4-tablet doses over 3 days) | 600 mg qd × 26 days | 12 | ↓ 21 ↓ 38 ↔ | ↓ 51 ↓ 46 ↓ 21 | NA NA NA
Atorvastatin Total active (including metabolites) | 10 mg qd x 4 days | 600 mg qd x 15 days | 14 | ↓ 14 (↓ 1 to ↓ 26) ↓ 15 (↓ 2 to ↓ 26) | ↓ 43 (↓ 34 to ↓ 50) ↓ 32 (↓ 21 to ↓ 41) | ↓ 69 (↓ 49 to ↓ 81) ↓ 48 (↓ 23 to ↓ 64)
Pravastatin | 40 mg qd x 4 days | 600 mg qd x 15 days | 13 | ↓ 32 (↓ 59 to ↑ 12) | ↓ 44 (↓ 26 to ↓ 57) | ↓ 19 (↓ 0 to ↓ 35)
Simvastatin Total active (including metabolites) | 40 mg qd x 4 days | 600 mg qd x 15 days | 14 | ↓ 72 (↓ 63 to ↓ 79) ↓ 68 (↓ 55 to ↓ 78) | ↓ 68 (↓ 62 to ↓ 73) ↓ 60 (↓ 52 to ↓ 68) | ↓ 45 (↓ 20 to ↓ 62) NAh
Carbamazepine Epoxide metabolite | 200 mg qd x 3 days, 200 mg bid x 3 days, then 400 mg qd x 29 days | 600 mg qd x 14 days | 12 | ↓ 20 (↓ 15 to ↓ 24) ↔ | ↓ 27 (↓ 20 to ↓ 33) ↔ | ↓ 35 (↓ 24 to ↓ 44) ↓ 13 (↓ 30 to ↑ 7)
Diltiazem Desacetyl diltiazem N-monodesmethyl diltiazem | 240 mg x 21 days | 600 mg qd x 14 days | 13 | ↓ 60 (↓ 50 to ↓ 68) ↓ 64 (↓ 57 to ↓ 69) ↓ 28 (↓ 7 to ↓ 44) | ↓ 69 (↓ 55 to ↓ 79) ↓ 75 (↓ 59 to ↓ 84) ↓ 37 (↓ 17 to ↓ 52) | ↓ 63 (↓ 44 to ↓ 75) ↓ 62 (↓ 44 to ↓ 75) ↓ 37 (↓ 17 to ↓ 52)
Ethinyl estradiol/ norgestimate Ethinyl estradiol Norelgestromin Levonorgestrel | 0.035 mg/0.25 mg x 14 days | 600 mg qd x 14 days
Ethinyl estradiol/ norgestimate Ethinyl estradiol Norelgestromin Levonorgestrel | 0.035 mg/0.25 mg x 14 days | 600 mg qd x 14 days | 21 | ↔ | ↔ | ↔
Ethinyl estradiol/ norgestimate Ethinyl estradiol Norelgestromin Levonorgestrel | 0.035 mg/0.25 mg x 14 days | 600 mg qd x 14 days | 21 | ↓ 46 (↓ 39 to ↓ 52) | ↓ 64 (↓ 62 to ↓ 67) | ↓ 82 (↓ 79 to ↓ 85)
Ethinyl estradiol/ norgestimate Ethinyl estradiol Norelgestromin Levonorgestrel | 0.035 mg/0.25 mg x 14 days | 600 mg qd x 14 days | 6 | ↓ 80 (↓ 77 to ↓ 83) | ↓ 83 (↓ 79 to ↓ 87) | ↓ 86 (↓ 80 to ↓ 90)
Methadone | Stable maintenance 35 to 100 mg daily | 600 mg qd x 14 to 21 days | 11 | ↓ 45 (↓ 25 to ↓ 59) | ↓ 52 (↓ 33 to ↓ 66) | NA
Bupropion Hydroxybupropion | 150 mg single dose (sustained- release) | 600 mg qd × 14 days | 13 | ↓ 34 (↓ 21 to ↓ 47) ↑ 50 (↑ 20 to ↑ 80) | ↓ 55 (↓ 48 to ↓ 62) ↔ | NA NA
Sertraline | 50 mg qd x 14 days | 600 mg qd x 14 days | 13 | ↓ 29 (↓ 15 to ↓ 40) | ↓ 39 (↓ 27 to ↓ 50) | ↓ 46 (↓ 31 to ↓ 58)
Voriconazole | 400 mg po q12h x 1 day then 200 mg po q12h x 8 days | 400 mg qd x 9 days | NA | ↓ 61i | ↓ 77i | NA
Voriconazole | 300 mg po q12h days 2 to 7 | 300 mg qd x 7 days | NA | ↓ 36j (↓ 21 to ↓ 49) | ↓ 55j (↓ 45 to ↓ 62) | NA
Voriconazole | 400 mg po q12h days 2 to 7 | 300 mg qd x 7 days | NA | ↑ 23j (↓ 1 to ↑ 53) | ↓ 7j (↓ 23 to ↑ 13) | NA
NA = not available
a. Increase = ↑; Decrease = ↓; No Effect = ↔
b. Compared with atazanavir 400 mg qd alone.
c. Comparator dose of indinavir was 800 mg q8h × 10 days.
d. Parallel-group design; N for EFV + lopinavir/ritonavir, N for lopinavir/ritonavir alone.
e. Values are for lopinavir. The pharmacokinetics of ritonavir 100 mg q12h are unaffected by concurrent EFV.
f. 95% CI
g. Soft Gelatin Capsule
h. Not available because of insufficient data.
i. 90% CI not available.
j. Relative to steady-state administration of voriconazole (400 mg for 1 day, then 200 mg po q12h for 2 days).
k. Study conducted with efavirenz, emtricitabine and tenofovir disoproxil fumarate coadministered with HARVONI.
l. The predominant circulating nucleoside metabolite of sofosbuvir.
m. Study conducted with efavirenz, emtricitabine and tenofovir disoproxil fumarate coadministered with SOVALDI® (sofosbuvir).
n. Study conducted with efavirenz, emtricitabine and tenofovir disoproxil fumarate coadministered with EPCLUSA.

Emtricitabine and Tenofovir DF: The steady-state pharmacokinetics of FTC and tenofovir were unaffected when FTC and TDF were administered together versus each agent dosed alone.

In vitro and clinical pharmacokinetic drug-drug interaction studies have shown that the potential for CYP mediated interactions involving FTC and tenofovir with other medicinal products is low.

TDF is a substrate of P-glycoprotein (P-gp) and breast cancer resistance protein (BCRP) transporters. When TDF is coadministered with an inhibitor of these transporters, an increase in absorption may be observed.

No clinically significant drug interactions have been observed between FTC and famciclovir, indinavir, sofosbuvir/velpatasvir, stavudine, TDF, and zidovudine. Similarly, no clinically significant drug interactions have been observed between TDF and abacavir, EFV, FTC, entecavir, indinavir, lamivudine, lopinavir/ritonavir, methadone, nelfinavir, oral contraceptives, ribavirin, saquinavir/ritonavir, sofosbuvir, or tacrolimus in trials conducted in healthy volunteers.

Following multiple dosing to HIV-negative subjects receiving either chronic methadone maintenance therapy, oral contraceptives, or single doses of ribavirin, steady-state tenofovir pharmacokinetics were similar to those observed in previous trials, indicating a lack of clinically significant drug interactions between these agents and TDF.

The effects of coadministered drugs on the Cmax, AUC, and Cmin of tenofovir are shown in Table 6. The effects of coadministration of TDF on Cmax, AUC, and Cmin of coadministered drugs are shown in Table 7.

Table 6 Drug Interactions: Changes in Pharmacokinetic Parameters for Tenofovir in the Presence of the Coadministered Druga,b
Coadministered Drug | Dose of Coadministered Drug (mg) | N | Mean % Change of Tenofovir Pharmacokinetic Parametersc (90% CI)
Coadministered Drug | Dose of Coadministered Drug (mg) | N | Cmax | AUC | Cmin
Atazanavird | 400 once daily x 14 days | 33 | ↑ 14 (↑ 8 to ↑ 20) | ↑ 24 (↑ 21 to ↑ 28) | ↑ 22 (↑ 15 to ↑ 30)
Atazanavir/ ritonavird | 300/100 once daily | 12 | ↑ 34 (↑ 20 to ↑ 51) | ↑ 37 (↑ 30 to ↑ 45) | ↑ 29 (↑ 21 to ↑ 36)
Darunavir/ ritonavire | 300/100 twice daily | 12 | ↑ 24 (↑ 8 to ↑ 42) | ↑ 22 (↑ 10 to ↑ 35) | ↑ 37 (↑ 19 to ↑ 57)
Didanosinef | 250 or 400 once daily × 7 days | 14 | ↔ | ↔ | ↔
Ledipasvir/ sofosbuvir | 90/400 once daily | 15 | ↑ 79 (↑ 56 to ↑ 104) | ↑ 98 (↑ 77 to ↑ 123) | ↑ 163 (↑ 132 to ↑ 197)
Lopinavir/ ritonavir | 400/100 twice daily × 14 days | 24 | ↔ | ↑ 32 (↑ 25 to ↑ 38) | ↑ 51 (↑ 37 to ↑ 66)
Sofosbuvir | 400 once daily | 16 | ↑ 25 (↑ 8 to ↑ 45) | ↔ | ↔
Sofosbuvir/ velpatasvir | 400/100 once daily | 15 | ↑ 77 (↑ 53 to ↑ 104) | ↑ 81 (↑ 68 to ↑ 94) | ↑ 121 (↑ 100 to ↑ 143)
Tipranavir/ ritonavirg | 500/100 twice daily | 22 | ↓ 23 (↓ 32 to ↓ 13) | ↓ 2 (↓ 9 to ↑ 5) | ↑ 7 (↓ 2 to ↑ 17)
Tipranavir/ ritonavirg | 750/200 twice daily (23 doses) | 20 | ↓ 38 (↓ 46 to ↓ 29) | ↑ 2 (↓ 6 to ↑ 10) | ↑ 14 (↑ 1 to ↑ 27)
a. All interaction trials conducted in healthy volunteers.
b. Subjects received TDF 300 mg once daily.
c. Increase = ↑; Decrease = ↓; No Effect = ↔
d. Reyataz Prescribing Information.
e. Prezista Prescribing Information.
f. Subjects received didanosine buffered tablets.
g. Aptivus Prescribing Information.

Table 7 Drug Interactions: Changes in Pharmacokinetic Parameters for Coadministered Drug in the Presence of TDFa,b
Coadministered Drug | Dose of Coadministered Drug (mg) | N | Mean % Change of Coadministered Drug Pharmacokinetic Parametersc (90% CI)
Coadministered Drug | Dose of Coadministered Drug (mg) | N | Cmax | AUC | Cmin
Atazanavird | 400 once daily x 14 days | 34 | ↓ 21 (↓ 27 to ↓ 14) | ↓ 25 (↓ 30 to ↓ 19) | ↓ 40 (↓ 48 to ↓ 32)
Atazanavird | Atazanavir/ritonavir 300/100 once daily x 42 days | 10 | ↓ 28 (↓ 50 to ↑ 5) | ↓ 25e (↓ 42 to ↓ 3) | ↓ 23e (↓ 46 to ↑ 10)
Darunavirf | Darunavir/ritonavir 300/100 once daily | 12 | ↑ 16 (↓ 6 to ↑ 42) | ↑ 21 (↓ 5 to ↑ 54) | ↑ 24 (↓ 10 to ↑ 69)
Didanosineg | 250 once, simultaneously with TDF and a light mealh | 33 | ↓ 20i (↓ 32 to ↓ 7) | ↔i | NA
Lopinavir Ritonavir | Lopinavir/ritonavir 400/100 twice daily x 14 days | 24 | ↔ | ↔ | ↔
Lopinavir Ritonavir | Lopinavir/ritonavir 400/100 twice daily x 14 days | 24 | ↔ | ↔ | ↔
Tipranavirj | Tipranavir/ritonavir 500/100 twice daily | 22 | ↓ 17 (↓ 26 to ↓ 6) | ↓ 18 (↓ 25 to ↓ 9) | ↓ 21 (↓ 30 to ↓ 10)
Tipranavirj | Tipranavir/ritonavir 750/200 twice daily (23 doses) | 20 | ↓ 11 (↓ 16 to ↓ 4) | ↓ 9 (↓ 15 to ↓ 3) | ↓ 12 (↓ 22 to 0)
a. All interaction trials conducted in healthy volunteers.
b. Subjects received TDF 300 mg once daily.
c. Increase = ↑; Decrease = ↓; No Effect = ↔
d. Reyataz Prescribing Information.
e. In HIV-infected patients, addition of TDF to atazanavir 300 mg plus ritonavir 100 mg, resulted in AUC and Cmin values of atazanavir that were 2.3- and 4-fold higher than the respective values observed for atazanavir 400 mg when given alone.
f. Prezista Prescribing Information.
g. Videx EC Prescribing Information. Subjects received didanosine enteric-coated capsules.
h. 373 kcal, 8.2 g fat.
i. Compared with didanosine (enteric-coated) 400 mg administered alone under fasting conditions.
j. Aptivus Prescribing Information.

12.4 Microbiology

Mechanism of Action
Efavirenz: EFV is a non-nucleoside reverse transcriptase (RT) inhibitor of HIV-1. Efavirenz activity is mediated predominantly by noncompetitive inhibition of HIV-1 reverse transcriptase. HIV-2 RT and human cellular DNA polymerases α, β, γ, and δ are not inhibited by EFV.
Emtricitabine: Emtricitabine, a synthetic nucleoside analog of cytidine, is phosphorylated by cellular enzymes to form FTC 5'-triphosphate. Emtricitabine 5'-triphosphate inhibits the activity of the HIV-1 RT by competing with the natural substrate deoxycytidine 5'-triphosphate and by being incorporated into nascent viral DNA which results in chain termination. Emtricitabine 5′-triphosphate is a weak inhibitor of mammalian DNA polymerases α, β, ε, and mitochondrial DNA polymerase γ.
Tenofovir DF: TDF is an acyclic nucleoside phosphonate diester analog of adenosine monophosphate. TDF requires initial diester hydrolysis for conversion to tenofovir and subsequent phosphorylations by cellular enzymes to form tenofovir diphosphate. Tenofovir diphosphate inhibits the activity of HIV-1 RT by competing with the natural substrate deoxyadenosine 5′-triphosphate and, after incorporation into DNA, by DNA chain termination. Tenofovir diphosphate is a weak inhibitor of mammalian DNA polymerases α, β, and mitochondrial DNA polymerase γ.
Antiviral Activity
Efavirenz, Emtricitabine, and Tenofovir DF: In combination studies evaluating the antiviral activity in cell culture of FTC and EFV together, EFV and tenofovir together, and FTC and tenofovir together, additive to synergistic antiviral effects were observed.
Efavirenz: The concentration of EFV inhibiting replication of wild-type laboratory adapted strains and clinical isolates in cell culture by 90 to 95% (EC90-95) ranged from 1.7 to 25 nM in lymphoblastoid cell lines, peripheral blood mononuclear cells, and macrophage/monocyte cultures. Efavirenz demonstrated additive antiviral activity against HIV-1 in cell culture when combined with non-nucleoside reverse transcriptase inhibitors (NNRTIs) (delavirdine and nevirapine), nucleoside reverse transcriptase inhibitors (NRTIs) (abacavir, didanosine, lamivudine, stavudine, zalcitabine, and zidovudine), protease inhibitors (PIs) (amprenavir, indinavir, lopinavir, nelfinavir, ritonavir, and saquinavir), and the fusion inhibitor enfuvirtide. Efavirenz demonstrated additive to antagonistic antiviral activity in cell culture with atazanavir. Efavirenz demonstrated antiviral activity against clade B and most non-clade B isolates (subtypes A, AE, AG, C, D, F, G, J, and N), but had reduced antiviral activity against group O viruses. Efavirenz is not active against HIV-2.
Emtricitabine: The antiviral activity in cell culture of FTC against laboratory and clinical isolates of HIV-1 was assessed in lymphoblastoid cell lines, the MAGI-CCR5 cell line, and peripheral blood mononuclear cells. The 50% effective concentration (EC50) values for FTC were in the range of 0.0013 to 0.64 µM (0.0003 to 0.158 mcg/mL). In drug combination studies of FTC with NRTIs (abacavir, lamivudine, stavudine, zalcitabine, and zidovudine), NNRTIs (delavirdine, EFV, and nevirapine), and PIs (amprenavir, nelfinavir, ritonavir, and saquinavir), additive to synergistic effects were observed. Emtricitabine displayed antiviral activity in cell culture against HIV-1 clades A, B, C, D, E, F, and G (EC50 values ranged from 0.007 to 0.075 µM) and showed strain-specific activity against HIV-2 (EC50 values ranged from 0.007 to 1.5 µM).
Tenofovir DF: The antiviral activity in cell culture of tenofovir against laboratory and clinical isolates of HIV-1 was assessed in lymphoblastoid cell lines, primary monocyte/macrophage cells and peripheral blood lymphocytes. The EC50 values for tenofovir were in the range of 0.04 to 8.5 µM. In drug combination studies of tenofovir with NRTIs (abacavir, didanosine, lamivudine, stavudine, zalcitabine, and zidovudine), NNRTIs (delavirdine, EFV, and nevirapine), and PIs (amprenavir, indinavir, nelfinavir, ritonavir, and saquinavir), additive to synergistic effects were observed. Tenofovir displayed antiviral activity in cell culture against HIV-1 clades A, B, C, D, E, F, G, and O (EC50 values ranged from 0.5 to 2.2 µM) and showed strain-specific activity against HIV-2 (EC50 values ranged from 1.6 to 5.5 µM).
Resistance
EFV, FTC, and TDF: HIV-1 isolates with reduced susceptibility to the combination of FTC and tenofovir have been selected in cell culture and in clinical trials. Genotypic analysis of these isolates identified the M184V/I and/or K65R amino acid substitutions in the viral RT. In addition, a K70E substitution in HIV-1 reverse transcriptase has been selected by tenofovir and results in reduced susceptibility to tenofovir.
In a clinical trial of treatment-naïve subjects [Study 934, see Clinical Studies (14)] resistance analysis was performed on HIV-1 isolates from all confirmed virologic failure subjects with greater than 400 copies/mL of HIV-1 RNA at Week 144 or early discontinuations. Genotypic resistance to EFV, predominantly the K103N substitution, was the most common form of resistance that developed. Resistance to EFV occurred in 13/19 analyzed subjects in the FTC + TDF group and in 21/29 analyzed subjects in the zidovudine/lamivudine fixed-dose combination group. The M184V amino acid substitution, associated with resistance to FTC and lamivudine, was observed in 2/19 analyzed subject isolates in the FTC + TDF group and in 10/29 analyzed subject isolates in the zidovudine/lamivudine group. Through 144 weeks of Study 934, no subjects developed a detectable K65R substitution in their HIV-1 as analyzed through standard genotypic analysis.
In a clinical trial of treatment-naïve subjects, isolates from 8/47 (17%) analyzed subjects receiving TDF developed the K65R substitution through 144 weeks of therapy; 7 of these occurred in the first 48 weeks of treatment and one at Week 96. In treatment experienced subjects, 14/304 (5%) of TDF treated subjects with virologic failure through Week 96 showed greater than 1.4-fold (median 2.7) reduced susceptibility to tenofovir. Genotypic analysis of the resistant isolates showed a substitution in the HIV-1 RT gene resulting in the K65R amino acid substitution.
Efavirenz: Clinical isolates with reduced susceptibility in cell culture to EFV have been obtained. The most frequently observed amino acid substitution in clinical trials with EFV is K103N (54%). One or more RT substitutions at amino acid positions 98, 100, 101, 103, 106, 108, 188, 190, 225, 227, and 230 were observed in subjects failing treatment with EFV in combination with other antiretrovirals. Other resistance substitutions observed to emerge commonly included L100I (7%), K101E/Q/R (14%), V108I (11%), G190S/T/A (7%), P225H (18%), and M230I/L (11%).
HIV-1 isolates with reduced susceptibility to EFV (greater than 380-fold increase in EC90 value) emerged rapidly under selection in cell culture. Genotypic characterization of these viruses identified substitutions resulting in single amino acid substitutions L100I or V179D, double substitutions L100I/V108I, and triple substitutions L100I/V179D/Y181C in RT.
Emtricitabine: Emtricitabine-resistant isolates of HIV-1 have been selected in cell culture and in clinical trials. Genotypic analysis of these isolates showed that the reduced susceptibility to FTC was associated with a substitution in the HIV-1 RT gene at codon 184 which resulted in an amino acid substitution of methionine by valine or isoleucine (M184V/I).
Tenofovir DF: HIV-1 isolates with reduced susceptibility to tenofovir have been selected in cell culture. These viruses expressed a K65R substitution in RT and showed a 2- to 4-fold reduction in susceptibility to tenofovir.
Cross Resistance
Efavirenz, Emtricitabine, and Tenofovir DF: Cross resistance has been recognized among NNRTIs. Cross resistance has also been recognized among certain NRTIs. The M184V/I and/or K65R substitutions selected in cell culture by the combination of FTC and tenofovir are also observed in some HIV-1 isolates from subjects failing treatment with tenofovir in combination with either lamivudine or FTC, and either abacavir or didanosine. Therefore, cross resistance among these drugs may occur in patients whose virus harbors either or both of these amino acid substitutions.
Efavirenz: Clinical isolates previously characterized as EFV resistant were also phenotypically resistant in cell culture to delavirdine and nevirapine compared to baseline. Delavirdine- and/or nevirapine-resistant clinical viral isolates with NNRTI resistance-associated substitutions (A98G, L100I, K101E/P, K103N/S, V106A, Y181X, Y188X, G190X, P225H, F227L, or M230L) showed reduced susceptibility to EFV in cell culture. Greater than 90% of NRTI-resistant isolates tested in cell culture retained susceptibility to EFV.
Emtricitabine: Emtricitabine-resistant isolates (M184V/I) were cross resistant to lamivudine but retained susceptibility in cell culture to didanosine, stavudine, tenofovir, zidovudine, and NNRTIs (delavirdine, EFV, and nevirapine). HIV-1 isolates containing the K65R substitution, selected in vivo by abacavir, didanosine, and tenofovir, demonstrated reduced susceptibility to inhibition by FTC. Viruses harboring substitutions conferring reduced susceptibility to stavudine and zidovudine (M41L, D67N, K70R, L210W, T215Y/F, and K219Q/E) or didanosine (L74V) remained sensitive to FTC.
Tenofovir DF: Cross resistance has been observed among NRTIs. The K65R substitution in HIV-1 RT selected by tenofovir is also selected in some HIV-1 infected patients treated with abacavir, or didanosine. HIV-1 isolates with the K65R substitution also showed reduced susceptibility to FTC and lamivudine. Therefore, cross resistance among these drugs may occur in patients whose virus harbors the K65R substitution. The K70E substitution selected clinically by TDF results in reduced susceptibility to abacavir, didanosine, FTC, and lamivudine. HIV-1 isolates from subjects (N=20) whose HIV-1 expressed a mean of 3 zidovudine-associated RT amino acid substitutions (M41L, D67N, K70R, L210W, T215Y/F, or K219Q/E/N) showed a 3.1-fold decrease in the susceptibility to tenofovir. Subjects whose virus expressed an L74V substitution without zidovudine resistance associated substitutions (N=8) had reduced response to TDF. Limited data are available for patients whose virus expressed a Y115F substitution (N=3), Q151M substitution (N=2), or T69 insertion (N=4), all of whom had a reduced response.

13 NONCLINICAL TOXICOLOGY

13.1 Carcinogenesis, Mutagenesis, Impairment of Fertility

Efavirenz: Long-term carcinogenicity studies in mice and rats were carried out with EFV. Mice were dosed with 0, 25, 75, 150, or 300 mg/kg/day for 2 years. Incidences of hepatocellular adenomas and carcinomas and pulmonary alveolar/bronchiolar adenomas were increased above background in females. No increases in tumor incidence above background were seen in males. In studies in which rats were administered EFV at doses of 0, 25, 50, or 100 mg/kg/day for 2 years, no increases in tumor incidence above background were observed. The systemic exposure (based on AUCs) in mice was approximately 1.7-fold that in humans receiving the 600 mg/day dose. The exposure in rats was lower than that in humans. The mechanism of the carcinogenic potential is unknown. However, in genetic toxicology assays, EFV showed no evidence of mutagenic or clastogenic activity in a battery of in vitro and in vivo studies. These included bacterial mutation assays in S. typhimurium and E. coli, mammalian mutation assays in Chinese hamster ovary cells, chromosome aberration assays in human peripheral blood lymphocytes or Chinese hamster ovary cells, and an in vivo mouse bone marrow micronucleus assay. Given the lack of genotoxic activity of EFV, the relevance to humans of neoplasms in EFV-treated mice is not known.
Efavirenz did not impair mating or fertility of male or female rats, and did not affect sperm of treated male rats. The reproductive performance of offspring born to female rats given EFV was not affected. Because of the rapid clearance of EFV in rats, systemic drug exposures achieved in these studies were equivalent to or below those achieved in humans given therapeutic doses of EFV.
Emtricitabine: In long-term carcinogenicity studies of FTC, no drug-related increases in tumor incidence were found in mice at doses up to 750 mg/kg/day (26 times the human systemic exposure at the therapeutic dose of 200 mg/day) or in rats at doses up to 600 mg/day (31 times the human systemic exposure at the therapeutic dose).
Emtricitabine was not genotoxic in the reverse mutation bacterial test (Ames test), or the mouse lymphoma or mouse micronucleus assays.
Emtricitabine did not affect fertility in male rats at approximately 140-fold or in male and female mice at approximately 60-fold higher exposures (AUC) than in humans given the recommended 200 mg daily dose. Fertility was normal in the offspring of mice exposed daily from before birth (in utero) through sexual maturity at daily exposures (AUC) of approximately 60-fold higher than human exposures at the recommended 200 mg daily dose.
Tenofovir DF: Long-term oral carcinogenicity studies of TDF in mice and rats were carried out at exposures up to approximately 16 times (mice) and 5 times (rats) those observed in humans at the therapeutic dose for HIV-1 infection. At the high dose in female mice, liver adenomas were increased at exposures 16 times that in humans. In rats, the study was negative for carcinogenic findings at exposures up to 5 times that observed in humans at the therapeutic dose.
TDF was mutagenic in the in vitro mouse lymphoma assay and negative in an in vitro bacterial mutagenicity test (Ames test). In an in vivo mouse micronucleus assay, TDF was negative when administered to male mice.
There were no effects on fertility, mating performance, or early embryonic development when TDF was administered to male rats at a dose equivalent to 10 times the human dose based on body surface area comparisons for 28 days prior to mating and to female rats for 15 days prior to mating through Day 7 of gestation. There was, however, an alteration of the estrous cycle in female rats.

13.2 Animal Toxicology and/or Pharmacology

Efavirenz: Nonsustained convulsions were observed in 6 of 20 monkeys receiving EFV at doses yielding plasma AUC values 4- to 13-fold greater than those in humans given the recommended dose.
Tenofovir DF: Tenofovir and TDF administered in toxicology studies to rats, dogs, and monkeys at exposures (based on AUCs) greater than or equal to 6-fold those observed in humans caused bone toxicity. In monkeys the bone toxicity was diagnosed as osteomalacia. Osteomalacia observed in monkeys appeared to be reversible upon dose reduction or discontinuation of tenofovir. In rats and dogs, the bone toxicity manifested as reduced bone mineral density. The mechanism(s) underlying bone toxicity is unknown.
Evidence of renal toxicity was noted in 4 animal species administered tenofovir and TDF. Increases in serum creatinine, BUN, glycosuria, proteinuria, phosphaturia and/or calciuria and decreases in serum phosphate were observed to varying degrees in these animals. These toxicities were noted at exposures (based on AUCs) 2- to 20-times higher than those observed in humans. The relationship of the renal abnormalities, particularly the phosphaturia, to the bone toxicity is not known.

14 CLINICAL STUDIES

Clinical Study 934 (NCT00112047) supports the use of efavirenz, emtricitabine and tenofovir disoproxil fumarate tablets in antiretroviral treatment-naïve HIV-1 infected patients.

Clinical Study 073 (NCT00365612) provides clinical experience in subjects with stable, virologic suppression and no history of virologic failure who switched from their current regimen to efavirenz, emtricitabine and tenofovir disoproxil fumarate.

In antiretroviral treatment-experienced patients, the use of efavirenz, emtricitabine and tenofovir disoproxil fumarate tablets may be considered for patients with HIV-1 strains that are expected to be susceptible to the components of efavirenz, emtricitabine and tenofovir disoproxil fumarate as assessed by treatment history or by genotypic or phenotypic testing [see Microbiology (12.4)].

Study 934: Data through 144 weeks are reported for Study 934, a randomized, open-label, active-controlled multicenter trial comparing FTC + TDF administered in combination with EFV versus zidovudine/lamivudine fixed-dose combination administered in combination with EFV in 511 antiretroviral-naïve subjects. From Weeks 96 to 144 of the trial, subjects received FTC/TDF fixed-dose combination with EFV in place of FTC + TDF with EFV. Subjects had a mean age of 38 years (range 18 to 80); 86% were male, 59% were Caucasian, and 23% were Black. The mean baseline CD4+ cell count was 245 cells/mm^3 (range 2 to 1191), and median baseline plasma HIV-1 RNA was 5.01 log10 copies/mL (range 3.56 to 6.54). Subjects were stratified by baseline CD4+ cell count (< or ≥200 cells/mm^3), and 41% had CD4+ cell counts <200 cells/mm^3. Fifty-one percent (51%) of subjects had baseline viral loads >100,000 copies/mL. Treatment outcomes through 48 and 144 weeks for those subjects who did not have EFV resistance at baseline (N=487) are presented in Table 8.

Table 8 Virologic Outcomes of Randomized Treatment at Weeks 48 and 144 (Study 934)
Outcomes | At Week 48 |  | At Week 144
Outcomes | FTC+TDF +EFV (N=244) | AZT/3TC +EFV (N=243) | FTC+TDF +EFV (N=227)a | AZT/3TC +EFV (N=229)a
Responderb | 84% | 73% | 71% | 58%
Virologic failurec | 2% | 4% | 3% | 6%
Rebound | 1% | 3% | 2% | 5%
Never suppressed | 0% | 0% | 0% | 0%
Change in antiretroviral regimen | 1% | 1% | 1% | 1%
Death | <1% | 1% | 1% | 1%
Discontinued due to adverse event | 4% | 9% | 5% | 12%
Discontinued for other reasonsd | 10% | 14% | 20% | 22%
a. Subjects who were responders at Week 48 or Week 96 (HIV-1 RNA <400 copies/mL) but did not consent to continue trial after Week 48 or Week 96 were excluded from analysis.
b. Subjects achieved and maintained confirmed HIV-1 RNA <400 copies/mL through Weeks 48 and 144.
c. Includes confirmed viral rebound and failure to achieve confirmed HIV-1 RNA <400 copies/mL through Weeks 48 and 144.
d. Includes lost to follow-up, patient withdrawal, noncompliance, protocol violation and other reasons.

Through Week 48, 84% and 73% of subjects in the FTC + TDF group and the zidovudine/lamivudine group, respectively, achieved and maintained HIV-1 RNA <400 copies/mL (71% and 58% through Week 144). The difference in the proportion of subjects who achieved and maintained HIV-1 RNA <400 copies/mL through 48 weeks largely results from the higher number of discontinuations due to adverse events and other reasons in the zidovudine/lamivudine group in this open-label trial. In addition, 80% and 70% of subjects in the FTC + TDF group and the zidovudine/lamivudine group, respectively, achieved and maintained HIV-1 RNA <50 copies/mL through Week 48 (64% and 56% through Week 144). The mean increase from baseline in CD4+ cell count was 190 cells/mm^3 in the FTC + TDF group and 158 cells/mm^3 in the zidovudine/lamivudine group at Week 48 (312 and 271 cells/mm^3 at Week 144).

Through 48 weeks, 7 subjects in the FTC + TDF group and 5 subjects in the zidovudine/lamivudine group experienced a new CDC Class C event (10 and 6 subjects through 144 weeks).

Study 073: Study 073 was a 48-week open-label, randomized clinical trial in subjects with stable virologic suppression on combination antiretroviral therapy consisting of at least two NRTIs administered in combination with a protease inhibitor (with or without ritonavir) or a NNRTI.

To be enrolled, subjects were to have HIV-1 RNA <200 copies/mL for at least 12 weeks on their current regimen prior to trial entry with no known HIV-1 substitutions conferring resistance to the components of efavirenz, emtricitabine and tenofovir disoproxil fumarateand no history of virologic failure.

The trial compared the efficacy of switching to efavirenz, emtricitabine and tenofovir disoproxil fumarate or staying on the baseline antiretroviral regimen (SBR). Subjects were randomized in a 2:1 ratio to switch to efavirenz, emtricitabine and tenofovir disoproxil fumarate(N=203) or stay on SBR (N=97). Subjects had a mean age of 43 years (range 22 to 73 years); 88% were male, 68% were white, 29% were Black or African-American, and 3% were of other races. At baseline, median CD4+ cell count was 516 cells/mm^3,and 96% had HIV-1 RNA <50 copies/mL. The median time since onset of antiretroviral therapy was 3 years, and 88% of subjects were receiving their first antiretroviral regimen at trial enrollment.

At Week 48, 89% and 87% of subjects who switched to efavirenz, emtricitabine and tenofovir disoproxil fumarate maintained HIV RNA <200 copies/mL and <50 copies/mL, respectively, compared to 88% and 85% who remained on SBR; this difference was not statistically significant. No changes in CD4+ cell counts from baseline to Week 48 were observed in either treatment arm.

16 HOW SUPPLIED/STORAGE AND HANDLING

Efavirenz, Emtricitabine and Tenofovir Disoproxil Fumarate Tablets are white to off-white, oval shaped, biconvex, film-coated tablets debossed with “I48” on one side and plain on the other side.

NDC: 72162-2565-3: 30 Tablets in a BOTTLE

Store at 20° to 25°C (68° to 77°F). [See USP Controlled Room Temperature.]

Keep container tightly closed.

Dispense only in original container.

Repackaged/Relabeled by:
Bryant Ranch Prepack, Inc.
Burbank, CA 91504

17 PATIENT COUNSELING INFORMATION

Advise the patient to read the FDA-approved patient labeling (Patient Information).

Severe Acute Exacerbation of Hepatitis B in Patients Coinfected with HIV-1 and HBV

Inform patients that severe acute exacerbations of hepatitis B have been reported in patients who are coinfected with HBV and HIV-1 and have discontinued FTC or TDF, and may occur with discontinuation of efavirenz, emtricitabine and tenofovir disoproxil fumarate tablets. Advise patients not to discontinue efavirenz, emtricitabine and tenofovir disoproxil fumarate tablets without first informing their healthcare provider. All patients should be tested for HBV infection before or when starting efavirenz, emtricitabine and tenofovir disoproxil fumarate tablets and those who are infected with HBV need close medical follow-up for several months after stopping efavirenz, emtricitabine and tenofovir disoproxil fumarate tablets to monitor for exacerbations of hepatitis [see Warnings and Precautions (5.1)].

Rash

Inform patients that a common side effect is rash, and that rashes usually go away without any change in treatment. However, since rash may be serious, advise patients to contact their physician promptly if rash occurs [see Warnings and Precautions (5.2)].

Hepatotoxicity

Inform patients to watch for early warning signs of liver inflammation or failure, such as fatigue, weakness, lack of appetite, nausea and vomiting, as well as later signs such as jaundice, confusion, abdominal swelling, and discolored feces, and to consult their health care professional without delay if such symptoms occur [see Warnings and Precautions (5.3) and Adverse Reactions (6.1)].

Drug Interactions

Advise patients that efavirenz, emtricitabine and tenofovir disoproxil fumarate tablets may interact with many drugs; therefore, advise patients to report to their healthcare provider the use of any other medication, including other drugs for treatment of hepatitis C virus [see Warnings and Precautions (5.4) and Drug Interactions (7)].

Psychiatric Symptoms

- Inform patients that serious psychiatric symptoms including severe depression, suicide attempts, aggressive behavior, delusions, paranoia, psychosis-like symptoms, and catatonia have been reported in patients receiving EFV, a component of efavirenz, emtricitabine and tenofovir disoproxil fumarate tablets [see Warnings and Precautions (5.5)].
- Advise patients to seek immediate medical evaluation if they experience severe psychiatric adverse experiences.
- Advise patients to inform their physician of any history of mental illness or substance abuse.

Nervous System Symptoms

- Inform patients that central nervous system symptoms (NSS) including dizziness, insomnia, impaired concentration, drowsiness, and abnormal dreams, are commonly reported during the first weeks of therapy with EFV, a component of efavirenz, emtricitabine and tenofovir disoproxil fumarate tablets. Dosing at bedtime may improve the tolerability of these symptoms, which are likely to improve with continued therapy.
- Alert patients to the potential for additive effects when efavirenz, emtricitabine and tenofovir disoproxil fumarate tablets are used concomitantly with alcohol or psychoactive drugs.
- Instruct patients that if they experience NSS to avoid potentially hazardous tasks such as driving or operating machinery [see Warnings and Precautions (5.6) and Dosage and Administration (2.2)].
- Inform patients that there is a risk of developing late-onset neurotoxicity, including ataxia and encephalopathy, which may occur months to years after beginning therapy with EFV, a component of efavirenz, emtricitabine and tenofovir disoproxil fumarate tablets [see Warnings and Precautions (5.6)].

New Onset or Worsening Renal Impairment

Inform patients that renal impairment, including cases of acute renal failure and Fanconi syndrome, has been reported. Advise patients to avoid using efavirenz, emtricitabine and tenofovir disoproxil fumarate tablets with concurrent or recent use of a nephrotoxic agent (e.g., high-dose or multiple NSAIDs) [see Warnings and Precautions (5.7)].

Embryo-Fetal Toxicity

Apprise patients of the potential harm to the fetus if efavirenz, emtricitabine and tenofovir disoproxil fumarate tablets are used during the first trimester of pregnancy, or if the patient becomes pregnant while taking this drug. Instruct adults and adolescents of childbearing potential receiving efavirenz, emtricitabine and tenofovir disoproxil fumarate tablets to avoid pregnancy and to notify their healthcare provider if they become pregnant or plan to become pregnant while taking efavirenz, emtricitabine and tenofovir disoproxil fumarate tablets [see Warnings and Precautions (5.8)]. A reliable form of barrier contraception must always be used in combination with other methods of contraception, including oral or other hormonal contraception. Because of the long half-life of EFV, recommend use of adequate contraceptive measures for 12 weeks after discontinuation of efavirenz, emtricitabine and tenofovir disoproxil fumarate tablets [see Use in Specific Populations (8.1, 8.3)].

Bone Loss and Mineralization Defects

Inform patients that decreases in bone mineral density have been observed with the use of TDF, a component of efavirenz, emtricitabine and tenofovir disoproxil fumarate tablets. Advise patients that bone mineral density monitoring may be performed in patients who have a history of pathologic bone fracture or other risk factors for osteoporosis or bone loss [see Warnings and Precautions (5.9)].

Convulsions

Inform patients that convulsions have been reported with the use of EFV, a component of efavirenz, emtricitabine and tenofovir disoproxil fumarate tablets. Patients who are receiving concomitant anticonvulsant medications primarily metabolized by the liver may require periodic monitoring of plasma levels [see Warnings and Precautions (5.10) and Drug Interactions (7.3)].

Lactic Acidosis and Severe Hepatomegaly

Inform patients that lactic acidosis and severe hepatomegaly with steatosis, including fatal cases, have been reported. Treatment with efavirenz, emtricitabine and tenofovir disoproxil fumarate tablets should be suspended in any patient who develops clinical symptoms suggestive of lactic acidosis or pronounced hepatotoxicity [see Warnings and Precautions (5.11)].

Immune Reconstitution Syndrome

Inform patients that in some patients with advanced HIV infection (AIDS), signs and symptoms of inflammation from previous infections may occur soon after anti-HIV treatment is started. It is believed that these symptoms are due to an improvement in the body’s immune response, enabling the body to fight infections that may have been present with no obvious symptoms. Advise patients to inform their healthcare provider immediately of any symptoms of infection [see Warnings and Precautions (5.12)].

Fat Redistribution

Inform patients that redistribution or accumulation of body fat may occur in patients receiving antiretroviral therapy, including efavirenz, emtricitabine and tenofovir disoproxil fumarate tablets and that the cause and long-term health effects of these conditions are not known [see Warnings and Precautions (5.13)].

Dosing Instructions

Advise patients to take efavirenz, emtricitabine and tenofovir disoproxil fumarate tablets orally on an empty stomach and that it is important to take efavirenz, emtricitabine and tenofovir disoproxil fumarate tablets on a regular dosing schedule to avoid missing doses. Advise patients that dosing at bedtime may improve the tolerability of nervous system symptoms [see Dosage and Administration (2.1)].

Pregnancy Registry

Advise patients that there is a pregnancy exposure registry that monitors pregnancy outcomes in patients exposed to efavirenz, emtricitabine and tenofovir disoproxil fumarate tablets during pregnancy [see Use in Specific Populations (8.1)].

Lactation

Instruct patients not to breastfeed because HIV-1 can be passed to the baby in the breast milk [see Use in Specific Populations (8.2)].

Patient Information

Efavirenz, Emtricitabine and Tenofovir Disoproxil Fumarate Tablets
(eh FAH vih renz, em tri SIT uh bean and te NOE’ fo veer dye soe PROX il FYOU mar ate)

What are the most important information I should know about efavirenz, emtricitabine and tenofovir disoproxil fumarate tablets?

Efavirenz, emtricitabine and tenofovir disoproxil fumarate tablets can cause serious side effects, including:

- Worsening of hepatitis B virus (HBV) infection. Your healthcare provider will test you for HBV before starting treatment with efavirenz, emtricitabine and tenofovir disoproxil fumarate tablets. If you have HBV infection and take efavirenz, emtricitabine and tenofovir disoproxil fumarate tablets, your HBV may get worse (flare-up) if you stop taking efavirenz, emtricitabine and tenofovir disoproxil fumarate tablets. A “flare-up” is when your HBV infection suddenly returns in a worse way than before.
  - Do not stop taking efavirenz, emtricitabine and tenofovir disoproxil fumarate tablets without first talking with your healthcare provider.
  - Do not run out of efavirenz, emtricitabine and tenofovir disoproxil fumarate tablets. Refill your prescription or talk to your healthcare provider before your efavirenz, emtricitabine and tenofovir disoproxil fumarate tablets are all gone.
  - If you stop taking efavirenz, emtricitabine and tenofovir disoproxil fumarate tablets, your healthcare provider will need to check your health often and do blood tests regularly for several months to check your HBV infection, or give you a medication to treat hepatitis B. Tell your healthcare provider about any new or unusual symptoms you may have after you stop taking efavirenz, emtricitabine and tenofovir disoproxil fumarate tablets.

For more information about side effects see the section,“What are the possible side effects of efavirenz, emtricitabine and tenofovir disoproxil fumarate tablets?”

What are efavirenz, emtricitabine and tenofovir disoproxil fumarate tablets?

Efavirenz, emtricitabine and tenofovir disoproxil fumarate tablet is a prescription medicine that contains efavirenz, emtricitabine, and tenofovir disoproxil fumarate combined in 1 tablet. Efavirenz, emtricitabine and tenofovir disoproxil fumarate tablets are used alone as a complete regimen, or in combination with other anti-HIV-1 medicines to treat people with HIV-1 infection who weigh at least 88 lbs (40 kg).

It is not known if efavirenz, emtricitabine and tenofovir disoproxil fumarate tablets are safe and effective for use in children with HIV-1 infection who weigh less than 88 lbs (40 kg).

Who should not take efavirenz, emtricitabine and tenofovir disoproxil fumarate tablets?

Do not take efavirenz, emtricitabine and tenofovir disoproxil fumarate tablets if you:

- are allergic to efavirenz
- take the medicine called voriconazole, elbasvir or grazoprevir

Ask your healthcare provider if you are not sure if you take any of these medicines.

Before taking efavirenz, emtricitabine and tenofovir disoproxil fumarate tablets, tell your healthcare provider about all of your medical conditions, including if you:

- have liver problems, including hepatitis B or C virus infection
- have heart problems
- have or have had mental problems
- have a history of drug or alcohol abuse
- have nervous system problems
- have kidney problems or receive kidney dialysis treatment
- have bone problems
- have had seizures or take medicines used to treat seizures
- are pregnant or plan to become pregnant. Efavirenz, emtricitabine and tenofovir disoproxil fumarate tablets can harm your unborn baby. If you are able to become pregnant, your healthcare provider should do a pregnancy test before you start treatment with efavirenz, emtricitabine and tenofovir disoproxil fumarate tablets. You should not become pregnant during treatment with efavirenz, emtricitabine and tenofovir disoproxil fumarate tablets and for 12 weeks after stopping treatment. Tell your healthcare provider if you become pregnant or think you may be pregnant during treatment with efavirenz, emtricitabine and tenofovir disoproxil fumarate tablets.
  - Females who are able to become pregnant should use 2 effective forms of birth control (contraception) during treatment with efavirenz, emtricitabine and tenofovir disoproxil fumarate tablets and for 12 weeks after stopping treatment.
  - A barrier form of birth control should always be used along with another type of birth control. Barrier forms of birth control may include condoms, contraceptive sponges, diaphragm with spermicide, and cervical cap.
  - Birth control methods that contain the hormone progesterone such as birth control pills, injections, vaginal rings, or implants, may not work as well while taking efavirenz, emtricitabine and tenofovir disoproxil fumarate tablets.
  - Talk to your healthcare provider about birth control methods that may be right for you during treatment with efavirenz, emtricitabine and tenofovir disoproxil fumarate tablets.
  - Pregnancy Registry: There is a pregnancy registry for women who take efavirenz, emtricitabine and tenofovir disoproxil fumarate tablets during pregnancy. The purpose of this registry is to collect information about the health of you and your baby. Talk to your healthcare provider about how you can take part in this registry.
- are breastfeeding or plan to breastfeed. Efavirenz, emtricitabine and tenofovir disoproxil fumarate can pass into your breast milk. Do not breastfeed because of the risk of passing HIV-1 to your baby.

Tell your healthcare provider about all the medicines you take, including prescription and over-the-counter medicines, vitamins and herbal supplements.

Keep a list of your medicines and show it to your healthcare provider and pharmacist when you get a new medicine.

Efavirenz, emtricitabine and tenofovir disoproxil fumarate tablets and some medicines may interact with each other causing serious side effects.

You can ask your healthcare provider or pharmacist for a list of medicines that interact with efavirenz, emtricitabine and tenofovir disoproxil fumarate tablets. Do not start a new medicine without telling your healthcare provider. Your healthcare provider can tell you if it is safe to take efavirenz, emtricitabine and tenofovir disoproxil fumarate tablets with other medicines.

How should I take efavirenz, emtricitabine and tenofovir disoproxil fumarate tablets?

- Take efavirenz, emtricitabine and tenofovir disoproxil fumarate tablets exactly as your healthcare provider tells you to.
- If you take efavirenz, emtricitabine and tenofovir disoproxil fumarate tablets with other medicines used to treat HIV-1, your healthcare provider will tell you what medicines to take and how to take them.
- Take efavirenz, emtricitabine and tenofovir disoproxil fumarate tablets 1 time each day on an empty stomach. You should take efavirenz, emtricitabine and tenofovir disoproxil fumarate tablets at the same time each day.
- Taking efavirenz, emtricitabine and tenofovir disoproxil fumarate tablets at bedtime may make some side effects less bothersome.
- Do not miss a dose of efavirenz, emtricitabine and tenofovir disoproxil fumarate tablets. Missing a dose lowers the amount of medicine in your blood. Refill your efavirenz, emtricitabine and tenofovir disoproxil fumarate tablets prescription before you run out of medicine.
- Do not change your efavirenz, emtricitabine and tenofovir disoproxil fumarate tablets dose or stop taking efavirenz, emtricitabine and tenofovir disoproxil fumarate tablets without first talking with your healthcare provider. Stay under a healthcare provider’s care during treatment with efavirenz, emtricitabine and tenofovir disoproxil fumarate tablets.
- If you take too much efavirenz, emtricitabine and tenofovir disoproxil fumarate, call your healthcare provider or got to the nearest hospital emergency room right away.

What should I avoid while taking efavirenz, emtricitabine and tenofovir disoproxil fumarate tablets?

- Efavirenz, emtricitabine and tenofovir disoproxil fumarate tablets can cause dizziness, impaired concentration and drowsiness. If you have these symptoms, do not drive a car, use heavy machinery, or do anything that requires you to be alert.

What are the possible side effects of efavirenz, emtricitabine and tenofovir disoproxil fumarate tablets?

Efavirenz, emtricitabine and tenofovir disoproxil fumarate tablets may cause serious side effects, including:

- See “What is the most important information I should know about efavirenz, emtricitabine and tenofovir disoproxil fumarate tablets?”
- Rash. Rash is a serious side effect but may also be common. Rashes will usually go away without any change in your treatment. Tell your healthcare provider right away if you develop a rash during treatment with efavirenz, emtricitabine and tenofovir disoproxil fumarate tablets.
- Severe liver problems. In rare cases, severe liver problems can happen that can lead to death. Tell your healthcare provider right away if you get these symptoms: skin or the white part of your eyes turns yellow, dark “tea-colored” urine, light-colored stools, loss of appetite for several days or longer, nausea, or stomach-area pain.
- Mental problems. Serious mental problems including severe depression, suicidal thoughts and actions, aggressive behavior, delusions, catatonia, and paranoid and manic reactions have happened in people who take efavirenz, emtricitabine and tenofovir disoproxil fumarate tablets. These mental health problems may happen more often in people who have a history of mental problems or drug use, or who take medicines to treat mental problems. Tell your healthcare provider right away if you develop serious mental problems during treatment with efavirenz, emtricitabine and tenofovir disoproxil fumarate tablets.

Nervous system problems. Nervous system problems usually begin during the first or second day of treatment with efavirenz, emtricitabine and tenofovir disoproxil fumarate tablets and usually go away after 2 to 4 weeks of treatment. Some symptoms may occur months to years after beginning efavirenz, emtricitabine and tenofovir disoproxil fumarate tablets therapy. These symptoms may become more severe if you drink alcohol or take mood altering (street) drugs while taking efavirenz, emtricitabine and tenofovir disoproxil fumarate tablets. Tell your healthcare provider right away if you develop nervous system problems during treatment with efavirenz, emtricitabine and tenofovir disoproxil fumarate tablets. Symptoms of nervous system problems may include:

- dizziness
- problems concentrating
- abnormal dreams
- unusually happy mood
- agitation
- thought problems
- slow thoughts and physical movement
- problems sleeping
- excessive sleepiness or difficulty awakening
- seeing or hearing things that are not real (hallucinations)
- confusion
- memory problems
- lack of coordination or difficulty with balance

If you have dizziness, trouble concentrating or sleepiness, do not drive a car, use machinery, or do anything that needs you to be alert.

- New or worse kidney problems, including kidney failure. Your healthcare provider should do blood and urine tests to check your kidneys before you start and during treatment with efavirenz, emtricitabine and tenofovir disoproxil fumarate tablets. Your healthcare provider may tell you to stop taking efavirenz, emtricitabine and tenofovir disoproxil fumarate tablets if you develop new or worse kidney problems during treatment with efavirenz, emtricitabine and tenofovir disoproxil fumarate tablets.
- Bone problems can happen in some people who take efavirenz, emtricitabine and tenofovir disoproxil fumarate tablets. Bone problems include bone pain or softening or thinning of bones, which may lead to fractures. Your healthcare provider may need to do tests to check your bones.
- Seizures. Your healthcare provider may do blood tests during treatment with efavirenz, emtricitabine and tenofovir disoproxil fumarate tablets if you take certain medicines used to prevent seizures.
- Too much lactic acid in your blood (lactic acidosis). Too much lactic acid is a serious but rare medical emergency that can lead to death. Tell your healthcare provider right away if you develop any of these symptoms:
  - weakness or being more tired than usual
  - being short of breath or fast breathing
  - cold or blue hands and feet
  - fast or abnormal heartbeat
  - unusual muscle pain
  - stomach pain with nausea and vomiting
  - feel dizzy or lightheaded
- Changes in your immune system (Immune Reconstitution Syndrome) can happen when an HIV-1 infected person starts taking HIV-1 medicines. Your immune system may get stronger and begin to fight infections that have been hidden in your body for a long time. Tell your healthcare provider right away if you develop any new symptoms after starting treatment with efavirenz, emtricitabine and tenofovir disoproxil fumarate tablets.
- Changes in body fat. Changes in body fat distribution or accumulation have happened in some people taking HIV-1 medicines, including an increased amount of fat in the upper back and neck ("buffalo hump"), in the breasts, and around the trunk. Loss of fat from the legs, arms, and face may also happen. The cause and long-term health effects of these body fat changes are not known.

The most common side effects of efavirenz, emtricitabine and tenofovir disoproxil fumarate tablets include:

- diarrhea
- tiredness
- dizziness
- problems sleeping
- rash
- nausea
- headache
- depression
- abnormal dreams

These are not all the possible side effects of efavirenz, emtricitabine and tenofovir disoproxil fumarate tablets.

Call your doctor for medical advice about side effects. You may report side effects to FDA at
1-800-FDA-1088.

How should I store efavirenz, emtricitabine and tenofovir disoproxil fumarate tablets?

- Store efavirenz, emtricitabine and tenofovir disoproxil fumarate tablets at room temperature between 68°F to 77°F (20°C to 25°C).
- Keep efavirenz, emtricitabine and tenofovir disoproxil fumarate tablets in its original container and keep the container tightly closed.

Keep efavirenz, emtricitabine and tenofovir disoproxil fumarate tablets and all other medicines out of reach of children.

General information about the safe and effective use of efavirenz, emtricitabine and tenofovir disoproxil fumarate tablets.

Medicines are sometimes prescribed for purposes other than those listed in a Patient Information leaflet. Do not use efavirenz, emtricitabine and tenofovir disoproxil fumarate tablets for a condition for which it was not prescribed. Do not give efavirenz, emtricitabine and tenofovir disoproxil fumarate tablets to other people, even if they have the same symptoms that you have. It may harm them. You can ask your healthcare provider or pharmacist for information about efavirenz, emtricitabine and tenofovir disoproxil fumarate tablets that is written for health professionals.

What are the ingredients of efavirenz, emtricitabine and tenofovir disoproxil fumarate tablets?

Active Ingredients: efavirenz, emtricitabine, and tenofovir disoproxil fumarate

Inactive Ingredients: croscarmellose sodium, hydroxypropyl cellulose, magnesium stearate, microcrystalline cellulose, and sodium lauryl sulfate. The film coating contains polyethylene glycol, polyvinyl alcohol, talc, and titanium dioxide.

Distributed by:
Aurobindo Pharma USA, Inc.
279 Princeton-Hightstown Road
East Windsor, NJ 08520

Manufactured by:
Aurobindo Pharma Limited
Hyderabad-500 032, India

Revised: 05/2023

For more information, call Aurobindo Pharma USA, Inc. at 1-866-850-2876.

The brands listed are the trademarks of their respective owners and are not trademarks of the Aurobindo Pharma Limited.

This Patient Information has been approved by the U.S. Food and Drug Administration.

PACKAGE LABEL

Efavirenz-Emtricitabine-Tenof 600-200-300